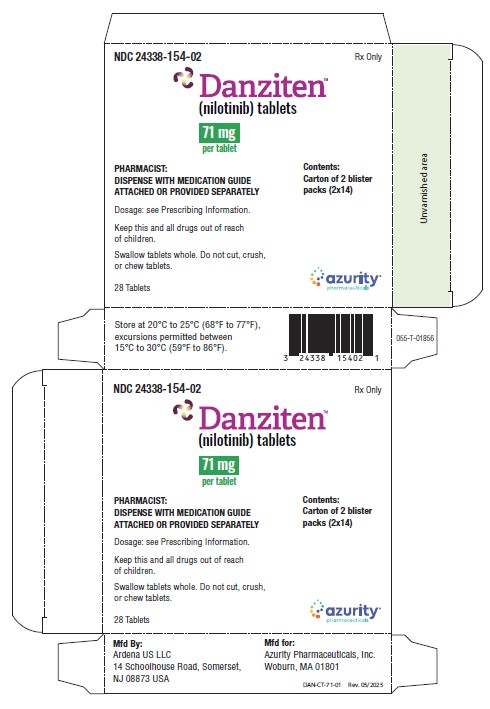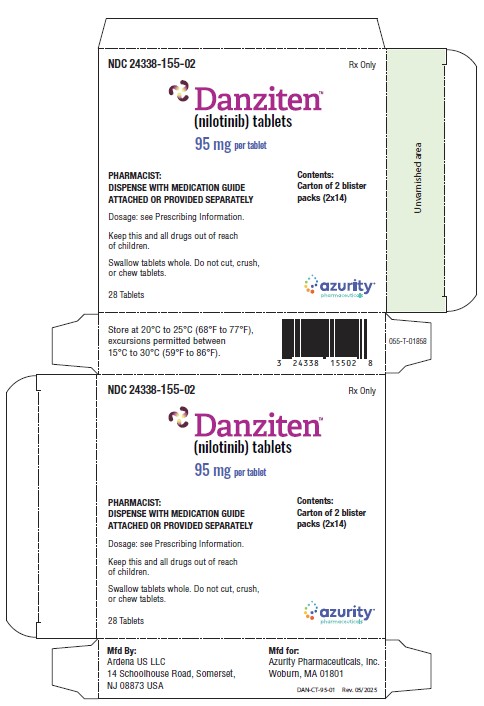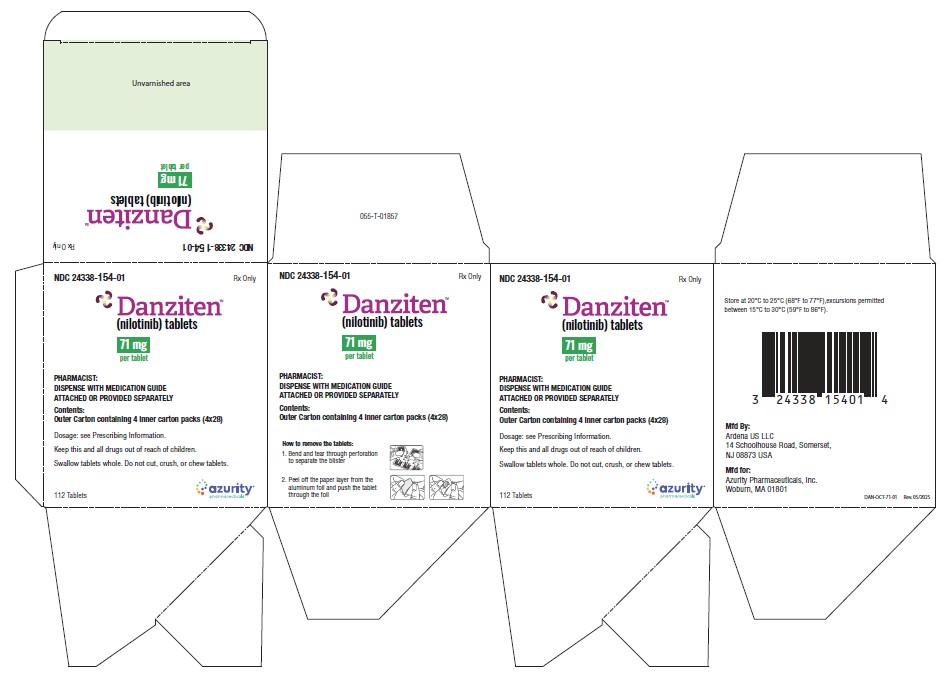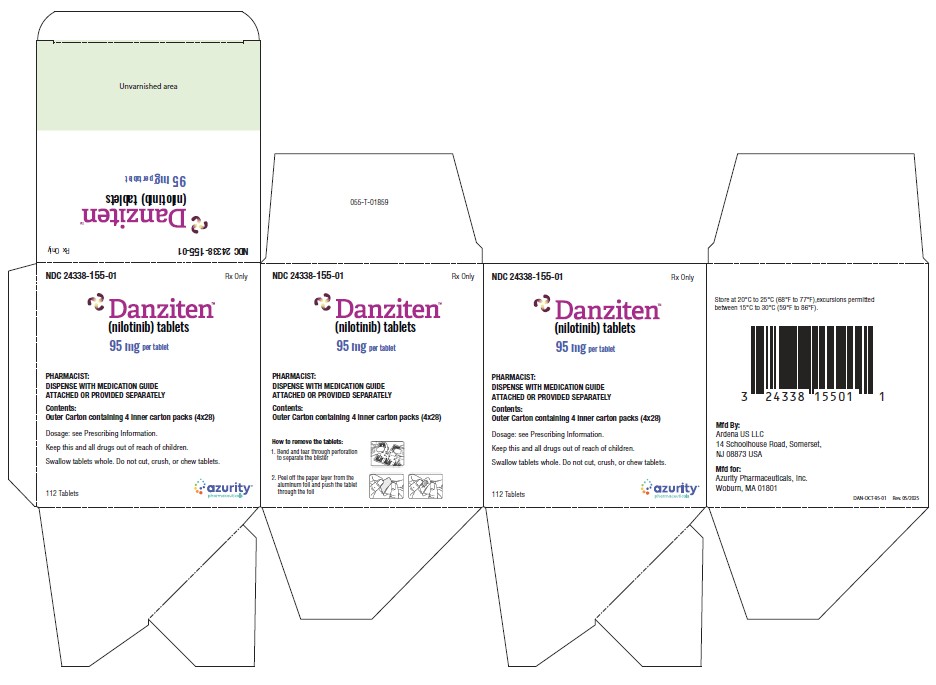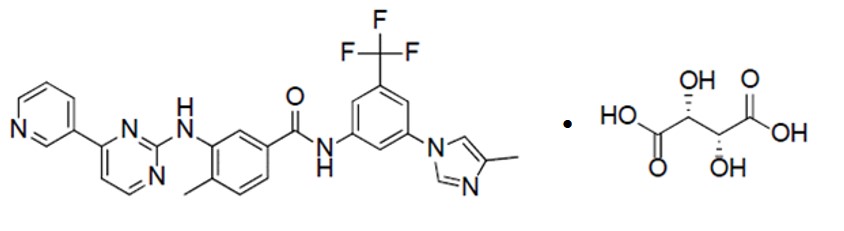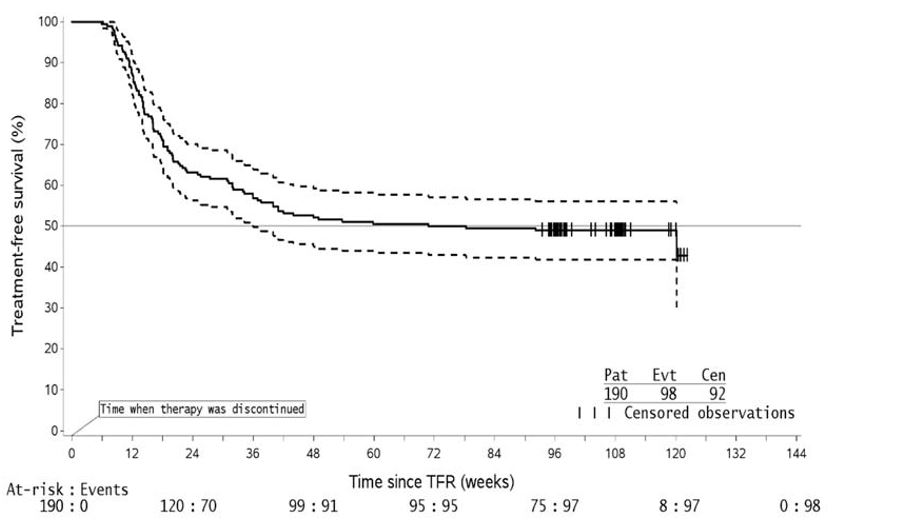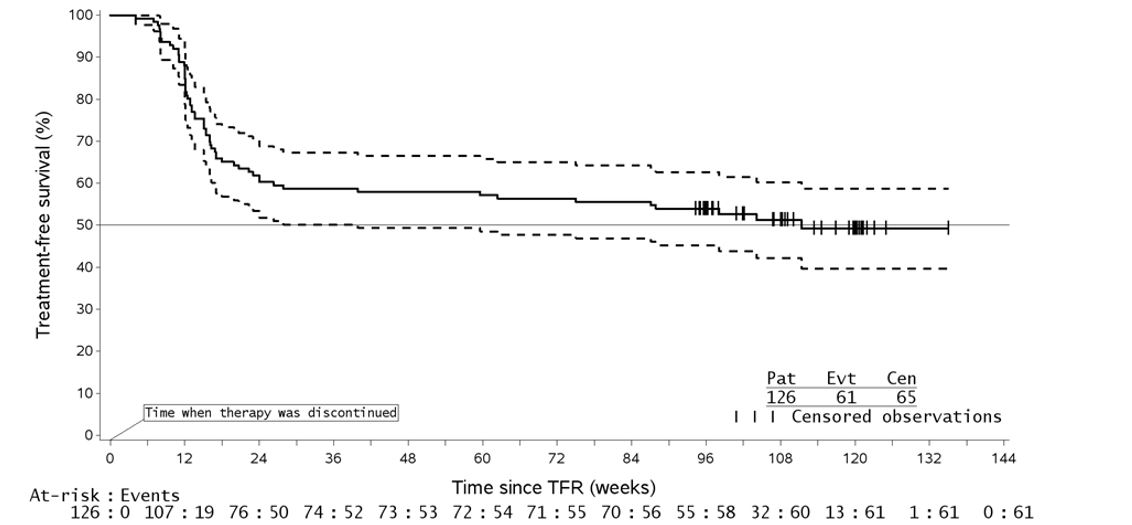 DRUG LABEL: DANZITEN
NDC: 24338-154 | Form: TABLET
Manufacturer: Azurity Pharmaceuticals, Inc.
Category: prescription | Type: Human Prescription Drug Label
Date: 20250728

ACTIVE INGREDIENTS: NILOTINIB 71 mg/1 1
INACTIVE INGREDIENTS: CROSCARMELLOSE SODIUM; HYPROMELLOSE ACETATE SUCCINATE 12070923 (3 MPA.S); CELLULOSE, MICROCRYSTALLINE; SILICON DIOXIDE; MAGNESIUM STEARATE; POLYVINYL ALCOHOL; POLYETHYLENE GLYCOL 3350; TITANIUM DIOXIDE

HIGHLIGHTS OF PRESCRIBING INFORMATION

These highlights do not include all the information needed to use DANZITEN safely and effectively. See full prescribing information for DANZITEN.
DANZITEN (nilotinib) tablets, for oral use
Initial U.S. Approval: 2007

WARNING: QT PROLONGATION and SUDDEN DEATHS

See full prescribing information for complete boxed warning.
• Nilotinib prolongs the QT interval. Prior to DANZITEN administration and periodically, monitor for hypokalemia or hypomagnesemia and correct deficiencies. (5.3) Obtain ECGs to monitor the QTc at baseline, seven days after initiation, and periodically thereafter, and following any dose adjustments. (5.3, 5.4, 5.8, 5.12)
• Sudden deaths have been reported in patients receiving nilotinib. (5.4) Do not administer DANZITEN to patients with hypokalemia, hypomagnesemia, or long QT syndrome. (4, 5.3)
• Avoid use of concomitant drugs known to prolong the QT interval and strong CYP3A4 inhibitors. (7.1, 7.2)

1 INDICATIONS AND USAGE

DANZITEN is a kinase inhibitor indicated for the treatment of:
• Adult patients with newly diagnosed Philadelphia chromosome positive chronic myeloid leukemia (Ph+ CML) in chronic phase. (1.1)
• Adult patients with chronic phase (CP) and accelerated phase (AP) Ph+ CML resistant to or intolerant to prior therapy that included imatinib. (1.2)

2 DOSAGE AND ADMINISTRATION

• To avoid medication errors and overdosage or under dosage, note that DANZITEN may have different strengths and dosages than other nilotinib products and may not be substitutable with other nilotinib products on a milligram per milligram basis. (2.1)
• Recommended Adult Dose:
• Newly diagnosed Ph+ CML-CP: 142 mg orally twice daily.
• Resistant or intolerant Ph+ CML-CP and CML-AP: 190 mg orally twice daily. (2.2)
• See Dosage and Administration for full dosing instructions and dose- reduction instructions for toxicity. (2.4, 2.5, 2.6, 2.7, 2.8, 2.9)
• Reduce starting dose in patients with baseline hepatic impairment. (2.8)
• Eligible newly diagnosed adult patients with Ph+ CML-CP who have received DANZITEN for a minimum of 3 years and have achieved a sustained molecular response (MR4.5) and patients with Ph+ CML-CP resistant or intolerant to imatinib who have received DANZITEN for at least 3 years and have achieved a sustained molecular response (MR4.5) may be considered for treatment discontinuation. (2.3, 2.4, 5.16)

3 DOSAGE FORMS AND STRENGTHS

Tablets: 71 mg, and 95 mg (3)

4 CONTRAINDICATIONS

DANZITEN is contraindicated in patients with hypokalemia, hypomagnesemia, or long QT syndrome. (4)

5 WARNINGS AND PRECAUTIONS

• Substitution with Other Nilotinib Products and Risk of Medication Errors: DANZITEN (nilotinib) tablets may not be substitutable with other nilotinib products, including other nilotinib tablets, on a milligram per milligram basis. Confirm that the intended nilotinib product is being prescribed and dispensed. (5.1)

• Myelosuppression: Monitor complete blood count (CBC) during therapy and manage by treatment interruption or dose reduction. (5.2)
• Cardiac and Arterial Vascular Occlusive Events: Evaluate cardiovascular status, monitor and manage cardiovascular risk factors during DANZITEN therapy. (5.5)
• Pancreatitis and Elevated Serum Lipase: Monitor serum lipase; if elevations are accompanied by abdominal symptoms, interrupt doses and consider appropriate diagnostics to exclude pancreatitis. (5.6)
• Hepatotoxicity: Monitor hepatic function tests monthly or as clinically indicated. (5.7)
• Electrolyte Abnormalities: DANZITEN can cause hypophosphatemia, hypokalemia, hyperkalemia, hypocalcemia, and hyponatremia. Correct electrolyte abnormalities prior to initiating DANZITEN and monitor periodically during therapy. (5.8)
• Tumor Lysis Syndrome: Maintain adequate hydration and correct uric acid levels prior to initiating therapy with DANZITEN. (5.9)
• Hemorrhage: Hemorrhage from any site may occur. Advise patients to report signs and symptoms of bleeding and medically manage as needed. (5.10)
• Fluid Retention: Monitor patients for unexpected rapid weight gain, swelling, and shortness of breath. Manage medically. (5.13)
• Effects on Growth and Development in Pediatric Patients: Growth retardation has been reported in pediatric patients treated with nilotinib. Monitor growth and development in pediatric patients. (5.14)
• Embryo-Fetal Toxicity: Can cause fetal harm. Advise females of reproductive potential of potential risk to a fetus and to use effective contraception. (5.15, 8.1,8.3)
• Treatment Discontinuation: Patients must have typical BCR-ABL transcripts. An FDA-authorized test with a detection limit below MR4.5 must be used to determine eligibility for discontinuation. Patients must be frequently monitored by the FDA authorized test to detect possible loss of remission. (5.16)

6 ADVERSE REACTIONS

The most commonly reported non-hematologic adverse reactions (≥ 20%) in adult patients are nausea, rash, headache, fatigue, pruritus, vomiting, diarrhea, cough, constipation, arthralgia, nasopharyngitis, pyrexia, and night sweats. Hematologic adverse drug reactions include myelosuppression: thrombocytopenia, neutropenia, and anemia. (6.1)
To report SUSPECTED ADVERSE REACTIONS, contact Azurity Pharmaceuticals, Inc., at 1-800-461-7449 or FDA at 1-800-FDA-1088 or www.fda.gov/medwatch.

7 DRUG INTERACTIONS

• Strong CYP3A Inhibitors: Avoid concomitant use with DANZITEN or reduce DANZITEN dose if concomitant use cannot be avoided. (7.1)
• Strong CYP3A Inducers: Avoid concomitant use with DANZITEN. (7.1)
• Proton Pump Inhibitors: Use short-acting antacids or H2 blockers as an alternative to proton pump inhibitors. (7.1)

8 USE IN SPECIFIC POPULATIONS

• Lactation: Advise women not to breastfeed. (8.2)

FULL PRESCRIBING INFORMATION

WARNING: QT PROLONGATION and SUDDEN DEATHS

• Nilotinib prolongs the QT interval. Prior to DANZITEN administration and periodically, monitor for hypokalemia or hypomagnesemia and correct deficiencies [see Warnings and Precautions (5.3)]. Obtain ECGs to monitor the QTc at baseline, seven days after initiation, and periodically thereafter, and following any dose adjustments [see Warnings and Precautions (5.3, 5.4, 5.8, 5.12)].
• Sudden deaths have been reported in patients receiving nilotinib [see Warnings and Precautions (5.4)]. Do not administer DANZITEN tablets to patients with hypokalemia, hypomagnesemia, or long QT syndrome [see Contraindications (4), Warnings and Precautions (5.3)].
• Avoid use of concomitant drugs known to prolong the QT interval and strong CYP3A4 inhibitors [see Drug Interactions (7.1, 7.2)].

1 INDICATIONS AND USAGE

1.1 Adult Patients with Newly Diagnosed Ph+ CML-CP

DANZITEN is indicated for the treatment of adult patients with newly diagnosed Philadelphia chromosome positive chronic myeloid leukemia (Ph+ CML) in chronic phase.
Additional pediatric use information is approved for Novartis Pharmaceuticals Corporation’s Tasigna® (nilotinib) capsules. However, due to Novartis Pharmaceuticals Corporation’s marketing exclusivity rights, this drug product is not labeled with that pediatric information.

1.2 Adult Patients with Resistant or Intolerant Ph+ CML-CP and CML-AP

DANZITEN is indicated for the treatment of adult patients with chronic phase and accelerated phase Philadelphia chromosome positive chronic myelogenous leukemia (Ph+ CML) resistant or intolerant to prior therapy that included imatinib.
Additional pediatric use information is approved for Novartis Pharmaceuticals Corporation’s Tasigna® (nilotinib) capsules. However, due to Novartis Pharmaceuticals Corporation’s marketing exclusivity rights, this drug product is not labeled with that pediatric information.

2 DOSAGE AND ADMINISTRATION

2.1 Important Use and Administration Instructions

• Nilotinib is available in different formulations, dosage forms, and strengths that are approved with different indications and recommended dosages.
• DANZITEN may not be substitutable with other nilotinib products on a milligram per milligram basis; to avoid medication errors, including overdosage or underdosage, when using DANZITEN ensure that the recommended dosage of DANZITEN (not the recommended dosage of other nilotinib products) is prescribed [see Dosage and Administration (2.2) and Warnings and Precautions (5.1)].
• When switching between DANZITEN (nilotinib) tablets and Tasigna (nilotinib) capsules, use the dosage conversion table [see Dosage and Administration (2.2)].

2.2 Recommended Dosage and Administration

Dosage in Adult Patients with Newly Diagnosed Ph+ CML-CP
The recommended dosage of DANZITEN is 142 mg orally twice daily at approximately 12-hour intervals with or without food [see Clinical Pharmacology (12.3)].
Dosage in Adult Patients with Resistant or Intolerant Ph+ CML-CP and CML-AP
The recommended dosage of DANZITEN is 190 mg orally twice daily at approximately 12-hour intervals with or without food [see Clinical Pharmacology (12.3)].
Additional Administration Instructions
Advise patients to swallow the tablets whole with water and not to cut, crush, or chew the tablets [see Boxed Warning]. If a dose of DANZITEN is missed, the patient should take the next scheduled dose at its regular time. The patient should not take two doses at the same time.
Switching Instructions
Use Table 1 when switching between DANZITEN and Tasigna based on dosage equivalence.

Table 1 Recommendations for Switching between DANZITEN and Tasigna

Approved Indications | DANZITEN dosage | Tasigna dosage
Newly diagnosed Ph+ CML-CP | 142 mg orally twice daily | 300 mg orally twice daily
Resistant or intolerant Ph+ CML-CP and CML-AP | 190 mg orally twice daily | 400 mg orally twice daily

Optional Concomitant Therapy

DANZITEN may be given in combination with hematopoietic growth factors, such as erythropoietin or G-CSF if clinically indicated. DANZITEN may be given with hydroxyurea or anagrelide if clinically indicated.

Additional pediatric use information is approved for Novartis Pharmaceuticals Corporation’s Tasigna (nilotinib) capsules. However, due to Novartis Pharmaceuticals Corporation’s marketing exclusivity rights, this drug product is not labeled with that pediatric information.

2.3 Discontinuation of Treatment After a Sustained Molecular Response (MR4.5) on DANZITEN

Patient Selection
Eligibility for Discontinuation of Treatment
Ph+ CML-CP patients with typical BCR-ABL transcripts, who have been taking DANZITEN for a minimum of 3 years and have achieved a sustained molecular response (MR4.5, corresponding to = BCR-ABL/ABL ≤ 0.0032% IS), may be eligible for treatment discontinuation [see Clinical Studies (14.3, 14.4)]. Information on FDA authorized tests for the detection and quantitation of BCR-ABL transcripts to determine eligibility for treatment discontinuation is available at http://www.fda.gov/CompanionDiagnostics.
Patients with typical BCR-ABL transcripts (e13a2/b2a2 or e14a2/b3a2), who achieve the sustained MR4.5 criteria, are eligible for discontinuation of DANZITEN. Patients must continue to be monitored for possible loss of molecular remission after treatment discontinuation. Use the same FDA-authorized test to consistently monitor molecular response levels while on and off treatment.
Consider discontinuation in patients with newly diagnosed Ph+ CML-CP who have:
• been treated with DANZITEN for at least 3 years
• maintained a molecular response of at least MR4.0 (corresponding to = BCR-ABL/ABL ≤ 0.01% IS) for one year prior to discontinuation of therapy
• achieved an MR4.5 for the last assessment taken immediately prior to discontinuation of therapy
• been confirmed to express the typical BCR-ABL transcripts (e13a2/b2a2 or e14a2/b3a2)
• no history of accelerated phase or blast crisis
• no history of prior attempts of treatment-free remission discontinuation that resulted in relapse.
Consider discontinuation in patients with Ph+ CML-CP that are resistant or intolerant to imatinib who have achieved a sustained molecular response (MR4.5) on DANZITEN who have:
• been treated with DANZITEN for a minimum of 3 years
• been treated with imatinib only prior to treatment with DANZITEN
• achieved a molecular response of MR4.5 (corresponding to = BCR-ABL/ABL ≤ 0.0032% IS)
• sustained an MR4.5 for a minimum of one year immediately prior to discontinuation of therapy
• been confirmed to express the typical BCR-ABL transcripts (e13a2/b2a2 or e14a2/b3a2)
• no history of accelerated phase or blast crisis
• no history of prior attempts of treatment-free remission discontinuation that resulted in relapse.
Monitor BCR-ABL transcript levels and complete blood count (CBC) with differential in patients who have discontinued DANZITEN therapy monthly for one year, then every 6 weeks for the second year, and every 12 weeks thereafter [see Warnings and Precautions (5.16)].
Upon the loss of MR4.0 (corresponding to = BCR-ABL/ABL ≤ 0.01% IS) during the treatment-free phase, monitor BCR-ABL transcript levels every 2 weeks until BCR-ABL levels remain lower than major molecular response [(MMR), corresponding to MR3.0 or = BCR-ABL/ABL ≤ 0.1% IS] for 4 consecutive measurements. The patient can then proceed to the original monitoring schedule.

2.4 Reinitiation of Treatment in Patients Who Lose Molecular Response After Discontinuation of Therapy with DANZITEN

• Newly diagnosed patients who lose MMR must reinitiate treatment within 4 weeks at the dose level prior to discontinuation of therapy [see Warnings and Precautions (5.16)]. Patients who reinitiate DANZITEN therapy should have their BCR-ABL transcript levels monitored monthly until major molecular response is re-established and every 12 weeks thereafter.
• Patients resistant or intolerant to prior treatment that included imatinib with confirmed loss of MR4.0 (2 consecutive measures separated by at least 4 weeks showing loss of MR4.0) or loss of MMR must reinitiate treatment within 4 weeks at the dose level prior to discontinuation of therapy [see Warnings and Precautions (5.16)]. Patients who reinitiate DANZITEN therapy should have their BCR-ABL transcript levels monitored monthly until previous major molecular response or MR4.0 is re-established and every 12 weeks thereafter.

2.5 Dosage Modification for QT Interval Prolongation

See Table 2 for dose adjustments for QT interval prolongation [see Warnings and Precautions (5.3) and Clinical Pharmacology (12.2)].

Table 2. Dosage Adjustments for Adult Patients with QT Prolongation

Degree of QTc Prolongation | Dosage Adjustment
ECGs with a QTc greater than 480 msec | 1. Withhold DANZITEN, and perform an analysis of serum potassium and magnesium, and if below lower limit of normal, correct with supplements to within normal limits. Concomitant medication usage must be reviewed. 2. Resume within 2 weeks at prior dose if QTcF returns to less than 450 msec and to within 20 msec of baseline. 3. If QTcF is between 450 msec and 480 msec after 2 weeks, reduce the dose to 190 mg once daily in adults. 4. Discontinue DANZITEN if, following dose-reduction to 190 mg once daily in adults, QTcF returns to greater than 480 msec. 5. An ECG should be repeated approximately 7 days after any dose adjustment.
Abbreviation: ECG, electrocardiogram.

Additional pediatric use information is approved for Novartis Pharmaceuticals Corporation’s Tasigna® (nilotinib) capsules. However, due to Novartis Pharmaceuticals Corporation’s marketing exclusivity rights, this drug product is not labeled with that pediatric information.

2.6 Dosage Modifications for Myelosuppression

Withhold or reduce DANZITEN dosage for hematological toxicities (neutropenia, thrombocytopenia) that are not related to underlying leukemia (Table 3) [see Warnings and Precautions (5.2)].

Table 3. Dosage Adjustments for Neutropenia and Thrombocytopenia

Diagnosis | Degree of Myelosuppression | Dosage Adjustment
Adult patients with: • Newly diagnosed Ph+ CML in chronic phase at 142 mg twice daily • Resistant or intolerant Ph+ CML in chronic phase or accelerated phase at 190 mg twice daily | ANC less than 1 x 10^9/L and/or platelet counts less than 50 x 10^9/L | 1. Stop DANZITEN and monitor blood counts. 2. Resume within 2 weeks at prior dose if ANC greater than 1 x 10^9/L and platelets greater than 50 x 10^9/L. 3. If blood counts remain low for greater than 2 weeks, reduce the dose to 190 mg once daily.
Abbreviations: ANC, absolute neutrophil count; Ph+ CML, Philadelphia chromosome positive chronic myeloid leukemia.

Additional pediatric use information is approved for Novartis Pharmaceuticals Corporation’s Tasigna® (nilotinib) capsules. However, due to Novartis Pharmaceuticals Corporation’s marketing exclusivity rights, this drug product is not labeled with that pediatric information.

2.7 Dosage Modifications for Selected Non-Hematologic Laboratory Abnormalities and Other Toxicities

See Table 4 for dosage adjustments for elevations of lipase, amylase, bilirubin, and/or hepatic transaminases. [see Warnings and Precautions (5.6, 5.7) and Adverse Reactions (6.1)].
Table 4. Dosage Adjustments for Selected Non-Hematologic Laboratory Abnormalities

Degree of Non- Hematologic Laboratory Abnormality | Dosage Adjustment
Elevated serum lipase or amylase greater than or equal to Grade 3 | Adult patients: 1. Withhold DANZITEN and monitor serum lipase or amylase. 2. Resume treatment at 190 mg once daily if serum lipase or amylase returns to less than or equal to Grade 1.
Elevated bilirubin greater than or equal to Grade 3 in adult patients | Adult patients: 1. Withhold DANZITEN and monitor bilirubin. 2. Resume treatment at 190 mg once daily if bilirubin returns to less than or equal to Grade 1.
Elevated hepatic transaminases greater than or equal to Grade 3 | Adult patients: 1. Withhold DANZITEN and monitor hepatic transaminases. 2. Resume treatment at 190 mg once daily if hepatic transaminases return to less than or equal to Grade 1.

If clinically significant moderate or severe non-hematologic toxicity develops (including medically severe fluid retention), see Table 5 for dosage adjustments [see Adverse Reactions (6.1)].

Table 5. Dosage Adjustments for Other Non-Hematologic Toxicities

Degree of “Other Non-Hematologic Toxicity” | Dosage Adjustment
Other clinically moderate or severe non- hematologic toxicity | Adult patients: 1. Withhold DANZITEN until toxicity has resolved. 2. Resume treatment at 190 mg once daily if previous dose was 142 mg twice daily in adult patients newly diagnosed with CML-CP or 190 mg twice daily in adult patients with resistant or intolerant CML-CP and CML-AP. 3. Discontinue treatment if the prior dose was 190 mg once daily in adult patients 4. If clinically appropriate, consider re-escalation of the dose to 142 mg (newly diagnosed Ph+ CML-CP) or 190 mg (resistant or intolerant Ph+ CML-CP and CML- AP) twice daily.
Abbreviations: CML-AP, chronic myeloid leukemia-accelerated phase; CML-CP, chronic myeloid leukemia-chronic phase; Ph+, Philadelphia chromosome positive.

Additional pediatric use information is approved for Novartis Pharmaceuticals Corporation’s Tasigna® (nilotinib) capsules. However, due to Novartis Pharmaceuticals Corporation’s marketing exclusivity rights, this drug product is not labeled with that pediatric information.

2.8 Recommended DANZITEN Dosage in Patients with Hepatic Impairment

If possible, consider alternative therapies. If DANZITEN must be administered to patients with hepatic impairment, the recommended DANZITEN dosage is provided in Table 6. [see Use in Specific Populations (8.7)]

Table 6. Recommended DANZITEN Dosage in Patients with Hepatic Impairment

Diagnosis | Degree of Hepatic Impairment | DANZITEN Dosage
Newly diagnosed Ph+ CML in chronic phase | Mild (Child-Pugh A), Moderate (Child-Pugh B), or Severe (Child- Pugh C) | Reduce DANZITEN dosage to 95 mg twice daily. Increase DANZITEN dosage to 142 mg twice daily based on tolerability.
Resistant or intolerant Ph+ CML in chronic phase or accelerated phase | Mild or Moderate | Reduce DANZITEN dosage to 142 mg twice daily. Increase DANZITEN dosage to 190 mg twice daily based on tolerability.
Resistant or intolerant Ph+ CML in chronic phase or accelerated phase | Severe | Reduce DANZITEN dosage to 95 mg twice daily. Increase DANZITEN dosage to 142 mg twice daily and then to 190 mg twice daily based on tolerability.

2.9 Dosage Modification for Strong CYP3A4 Inhibitors

Avoid the concomitant use of strong CYP3A4 inhibitors. Should treatment with any of these agents be required, interrupt therapy with DANZITEN.
If concomitant use is required, reduce DANZITEN dosage to 142 mg once daily in patients with resistant or intolerant Ph+ CML or to 95 mg once daily in patients with newly diagnosed Ph+ CML-CP. If the strong inhibitor is discontinued, allow a washout period of 5 half-lives before adjusting DANZITEN dose upward to the indicated dose. For patients who cannot avoid use of strong CYP3A4 inhibitors, monitor closely for prolongation of the QT interval [see Boxed Warning, Warnings and Precautions (5.3), Drug Interactions (7.1, 7.2), Clinical Pharmacology (12.3)].

3 DOSAGE FORMS AND STRENGTHS

Tablets:
• 71 mg: pink coated oblong tablets, debossed with “N5” on one side and plain on other side. Each tablet contains 71 mg of nilotinib.
• 95 mg: yellow coated oblong tablets, debossed with “N2” on one side and plain on other side. Each tablet contains 95 mg of nilotinib.

4 CONTRAINDICATIONS

DANZITEN is contraindicated in patients with hypokalemia, hypomagnesemia, or long QT syndrome [see Boxed Warning and Warnings and Precautions (5.3)].

5 WARNINGS AND PRECAUTIONS

5.1 Substitution with Other Nilotinib Products and Risk of Medication Errors

Nilotinib is available in different formulations, recommended dosages, and tablet strengths, and for different indications. DANZITEN (nilotinib) tablets may not be substitutable with other nilotinib products, including other nilotinib tablets, on a milligram per milligram basis. When switching patients between other nilotinib products and DANZITEN (nilotinib) tablets, a dose conversion may be required [see Dosage and Administration (2.1 and 2.2)]. Substitution of DANZITEN (nilotinib) tablets for another nilotinib product to achieve the same daily nilotinib dosage on a milligram per milligram basis may result in a clinically significant:
• Increase in nilotinib exposure which may increase the risk of nilotinib-associated adverse reactions.
• Decrease in nilotinib exposure which may reduce DANZITEN effectiveness.
Confirm that the intended nilotinib product is being prescribed and dispensed.

5.2 Myelosuppression

Treatment with DANZITEN can cause Grade 3/4 thrombocytopenia, neutropenia, and anemia. Perform CBCs every 2 weeks for the first 2 months and then monthly thereafter, or as clinically indicated. Myelosuppression was generally reversible and usually managed by withholding DANZITEN temporarily or dose reduction [see Dosage and Administration (2.6)].

5.3 QT Prolongation

Nilotinib has been shown to prolong cardiac ventricular repolarization as measured by the QT interval on the surface electrocardiogram (ECG) in a concentration-dependent manner [see Adverse Reactions (6.1), Clinical Pharmacology (12.2)]. Prolongation of the QT interval can result in a type of ventricular tachycardia called torsade de pointes, which may result in syncope, seizure, and/or death. Electrocardiograms should be performed at baseline, 7 days after initiation of DANZITEN, and periodically as clinically indicated and following dose adjustments [see Dosage and Administration (2.5) and Warnings and Precautions (5.12)].
DANZITEN should not be used in patients who have hypokalemia, hypomagnesemia, or long QT syndrome. Before initiating DANZITEN and periodically, test electrolyte, calcium, and magnesium blood levels. Hypokalemia or hypomagnesemia must be corrected prior to initiating DANZITEN and these electrolytes should be monitored periodically during therapy [see Warnings and Precautions (5.12)].
Significant prolongation of the QT interval may occur when DANZITEN is inappropriately taken with strong CYP3A4 inhibitors and/or medicinal products with a known potential to prolong QT. Therefore, avoid concomitant DANZITEN use with strong CYP3A4 inhibitors and/or medicinal products with a known potential to prolong QT [see Dosage and Administration (2.9), Drug Interactions (7.1, 7.2)]. The presence of hypokalemia and hypomagnesemia may further prolong the QT interval [see Warnings and Precautions (5.8, 5.12)].

5.4 Sudden Deaths

Sudden deaths have been reported in 0.3% of patients with CML treated with nilotinib in clinical studies of 5661 patients. The relative early occurrence of some of these deaths relative to the initiation of nilotinib suggests the possibility that ventricular repolarization abnormalities may have contributed to their occurrence.

5.5 Cardiac and Arterial Vascular Occlusive Events

Cardiovascular events, including arterial vascular occlusive events, were reported in a randomized, clinical trial in newly diagnosed CML patients and observed in the postmarketing reports of patients receiving nilotinib therapy [see Adverse Reactions (6.1)]. With a median time on therapy of 60 months in the clinical trial, cardiovascular events, including arterial vascular occlusive events, occurred in 9% and 15% of patients receiving nilotinib dosages equivalent to DANZITEN 142 mg and 190 mg twice daily, respectively, and in 3.2% in the imatinib arm. These included cases of cardiovascular events, including ischemic heart disease-related cardiac events (5% and 9% in the nilotinib dosages equivalent to DANZITEN 142 mg and 190 mg twice daily, respectively and 2.5% in the imatinib arm), peripheral arterial occlusive disease (3.6% and 2.9% in the nilotinib dosages equivalent to DANZITEN 142 mg and 190 mg twice daily, respectively and 0% in the imatinib arm), and ischemic cerebrovascular events (1.4% and 3.2% in the nilotinib dosages equivalent to DANZITEN 142 mg and 190 mg twice daily, respectively and 0.7% in the imatinib arm). If acute signs or symptoms of cardiovascular events occur, advise patients to seek immediate medical attention. The cardiovascular status of patients should be evaluated, and cardiovascular risk factors should be monitored and actively managed during DANZITEN therapy according to standard guidelines [see Dosage and Administration (2.5)].

5.6 Pancreatitis and Elevated Serum Lipase

Nilotinib can cause increases in serum lipase [see Adverse Reactions (6.1)]. Patients with a previous history of pancreatitis may be at greater risk of elevated serum lipase. If lipase elevations are accompanied by abdominal symptoms, interrupt dosing and consider appropriate diagnostics to exclude pancreatitis [see Dosage and Administration (2.7)]. Test serum lipase levels monthly or as clinically indicated.

5.7 Hepatotoxicity

Nilotinib may result in hepatotoxicity as measured by elevations in bilirubin, aspartate aminotransferase (AST), alanine aminotransferase (ALT), and alkaline phosphatase. Grade 3-4 elevations of bilirubin, AST, and ALT were reported in adult patients. Grade 3-4 elevations of bilirubin, AST, and ALT were reported at a higher frequency in pediatric than in adult patients. Monitor hepatic function tests monthly or as clinically indicated [see Warnings and Precautions (5.12)] and following dose adjustments. [see Dosage and Administration (2.8)].

5.8 Electrolyte Abnormalities

The use of nilotinib can cause hypophosphatemia, hypokalemia, hyperkalemia, hypocalcemia, and hyponatremia. Correct electrolyte abnormalities prior to initiating DANZITEN and during therapy. Monitor these electrolytes periodically during therapy [see Warnings and Precautions (5.12)].

5.9 Tumor Lysis Syndrome

Tumor lysis syndrome (TLS) cases have been reported in nilotinib treated patients with resistant or intolerant CML. Malignant disease progression, high white blood cell (WBC) counts and/or dehydration were present in the majority of these cases. Due to potential for TLS, maintain adequate hydration and correct uric acid levels prior to initiating therapy with DANZITEN.

5.10 Hemorrhage

Serious hemorrhagic events, including fatal events, have occurred in patients with CML treated with nilotinib. In a randomized trial in patients with newly diagnosed Ph+ CML in chronic phase comparing nilotinib and imatinib, Grade 3 or 4 hemorrhage occurred in 1.1% of patients in the nilotinib dosage equivalent to DANZITEN 142 mg twice daily arm, in 1.8% of patients in the nilotinib dosage equivalent to DANZITEN 190 mg twice daily arm, and 0.4% of patients in the imatinib arm. GI hemorrhage occurred in 2.9% and 5% of patients in the nilotinib dosage equivalent DANZITEN 142 mg and 190 mg twice daily arms and in 1.4% of patients in the imatinib arm, respectively. Grade 3 or 4 events occurred in 0.7% and 1.4% of patients in the nilotinib dosage equivalent to DANZITEN 142 mg and 190 mg twice daily arms, respectively, and in no patients in the imatinib arm. Monitor for signs and symptoms of bleeding and medically manage as needed.

5.11 Total Gastrectomy

Since the exposure of nilotinib is reduced in patients with total gastrectomy, perform more frequent monitoring of these patients. Consider dose increase or alternative therapy in patients with total gastrectomy [see Clinical Pharmacology (12.3)].

5.12 Monitoring Laboratory Tests

Complete blood counts should be performed every 2 weeks for the first 2 months and then monthly thereafter. Perform chemistry panels, including electrolytes, calcium, magnesium, liver enzymes, lipid profile, and glucose prior to therapy and periodically. Electrocardiograms should be obtained at baseline, 7 days after initiation and periodically thereafter, as well as following dose adjustments [see Warnings and Precautions (5.3)]. Monitor lipid profiles and glucose periodically during the first year of DANZITEN therapy and at least yearly during chronic therapy. Should treatment with any HMG-CoA reductase inhibitor (a lipid lowering agent) be needed to treat lipid elevations, evaluate the potential for a drug-drug interaction before initiating therapy as certain HMG-CoA reductase inhibitors are metabolized by the CYP3A4 pathway [see Drug Interactions (7.1)]. Assess glucose levels before initiating treatment with DANZITEN and monitor during treatment as clinically indicated. If test results warrant therapy, physicians should follow their local standards of practice and treatment guidelines.

5.13 Fluid Retention

In the randomized trial in patients with newly diagnosed Ph+ CML in chronic phase, severe (Grade 3 or 4) fluid retention occurred in 3.9% and 2.9% of patients receiving the nilotinib dosage equivalent to DANZITEN 142 mg and 190 mg twice daily, respectively, and in 2.5% of patients receiving imatinib. Effusions (including pleural effusion, pericardial effusion, ascites) or pulmonary edema, were observed in 2.2% and 1.1% of patients receiving the nilotinib dosage equivalent to the recommended dosage of DANZITEN 142 mg twice daily and 190 mg twice daily, respectively, and in 2.1% of patients receiving imatinib. Effusions were severe (Grade 3 or 4) in 0.7% and 0.4% of patients receiving the nilotinib dosage equivalent to the recommended dosage of DANZITEN 142 mg and 190 mg twice daily, respectively, and in no patients receiving imatinib. Similar events were also observed in postmarketing reports. Monitor patients for signs of severe fluid retention (e.g., unexpected rapid weight gain or swelling) and for symptoms of respiratory or cardiac compromise (e.g., shortness of breath) during DANZITEN treatment; evaluate etiology and treat patients accordingly.

5.14 Effects on Growth and Development

Growth retardation has been reported in pediatric patients with Ph+ CML in chronic phase treated with nilotinib. Growth deceleration was more pronounced in children who were less than age 12 at baseline. Monitor growth and development in pediatric patients receiving nilotinib treatment.
Additional pediatric use information is approved for Novartis Pharmaceuticals Corporation’s Tasigna® (nilotinib) capsules. However, due to Novartis Pharmaceuticals Corporation’s marketing exclusivity rights, this drug product is not labeled with that pediatric information.

5.15 Embryo-Fetal Toxicity

Based on findings from animal studies and its mechanism of action, DANZITEN can cause fetal harm when administered to a pregnant woman. In animal reproduction studies, administration of nilotinib to pregnant rats and rabbits during organogenesis caused adverse developmental outcomes, including embryo-fetal lethality/fetal effects (small renal papilla, fetal edema, and skeletal variations) in rats and increased resorptions of fetuses and fetal skeletal variations in rabbits at maternal area under the curve (AUCs) approximately 2 and 0.5 times, respectively, the AUC in patients receiving the recommended dose.
Advise pregnant women of the potential risk to a fetus. Advise females of reproductive potential to use effective contraception during treatment and for 14 days after the last dose [see Use in Specific Populations (8.1, 8.3), Clinical Pharmacology (12.1)].

5.16 Monitoring of BCR-ABL Transcript Levels

Monitoring of BCR-ABL Transcript Levels in Patients Who Discontinued Nilotinib
Monitor BCR-ABL transcript levels in patients eligible for treatment discontinuation using an FDA authorized test validated to measure molecular response levels with a sensitivity of at least MR4.5 (BCR-ABL/ABL ≤ 0.0032% IS). In patients who discontinue DANZITEN therapy, assess BCR-ABL transcript levels monthly for one year, then every 6 weeks for the second year, and every 12 weeks thereafter during treatment discontinuation [see Clinical Studies (14.3,14.4), Dosage and Administration (2.3)].
Newly diagnosed patients must reinitiate DANZITEN therapy within 4 weeks of a loss of major molecular response [(MMR), corresponding to MR3.0 or = BCR-ABL/ABL ≤ 0.1% IS].
Patients resistant or intolerant to prior treatment which included imatinib must reinitiate DANZITEN therapy within 4 weeks of a loss of MMR or confirmed loss of MR4.0 (two consecutive measures separated by at least 4 weeks showing loss of MR4.0, corresponding to = BCR-ABL/ABL ≤ 0.01% IS).
For patients who fail to achieve MMR after three months of treatment reinitiation, BCR-ABL kinase domain mutation testing should be performed.
Monitoring of BCR-ABL Transcript Levels in Patients Who Have Reinitiated Therapy After Loss of Molecular Response
Monitor CBC and BCR-ABL transcripts in patients who reinitiate treatment with DANZITEN due to loss of molecular response quantitation every 4 weeks until a major molecular response is re-established, then every 12 weeks [see Dosage and Administration (2.4)].

6 ADVERSE REACTIONS

The following clinically significant adverse reactions can occur with DANZITEN and are discussed in greater detail in other sections of labeling:
• Myelosuppression [see Warnings and Precautions (5.2)]
• QT Prolongation [see Boxed Warning, Warnings and Precautions (5.3)]
• Sudden Deaths [see Boxed Warning, Warnings and Precautions (5.4)]
• Cardiac and Arterial Vascular Occlusive Events [see Warnings and Precautions (5.5)]
• Pancreatitis and Elevated Serum Lipase [see Warnings and Precautions (5.6)]
• Hepatotoxicity [see Warnings and Precautions (5.7)]
• Electrolyte Abnormalities [see Boxed Warning, Warnings and Precautions (5.8)]
• Hemorrhage [see Warnings and Precautions (5.10)]
• Fluid Retention [see Warnings and Precautions (5.13)]

6.1 Clinical Trials Experience

Because clinical trials are conducted under widely varying conditions, adverse reaction rates observed in the clinical trials of a drug cannot be directly compared to rates in the clinical trials of another drug and may not reflect the rates observed in practice.
The safety of DANZITEN (nilotinib) tablets has been established from adequate and well-controlled studies of Tasigna® (nilotinib) capsules, which has different recommended dosages than DANZITEN, in adult patients with newly diagnosed Philadelphia chromosome positive chronic myeloid leukemia (Ph+ CML) in chronic phase (CP) and adult patients with CP and accelerated phase (AP) Ph+ CML resistant to or intolerant to prior therapy that included imatinib [see Clinical Studies (14)]. Below is a display of the adverse reactions of Tasigna® (nilotinib) capsules in these adequate and well-controlled studies.
In Adult Patients With Newly Diagnosed Ph+ CML-CP
The data below reflect exposure to nilotinib from a randomized trial in patients with newly diagnosed Ph+ CML in chronic phase treated at the equivalent recommended dosage of DANZITEN 142 mg twice daily (n = 279). The median time on treatment at the equivalent recommended dosage of DANZITEN 142 mg twice daily group was 61 months (range, 0.1 to 71 months).
The most common (greater than 10%) non-hematologic adverse drug reactions were rash, pruritus, headache, nausea, fatigue, alopecia, myalgia, and upper abdominal pain. Constipation, diarrhea, dry skin, muscle spasms, arthralgia, abdominal pain, peripheral edema, vomiting, and asthenia were observed less commonly (less than or equal to 10% and greater than 5%).
Increase in QTcF greater than 60 msec from baseline was observed in 1 patient (0.4%) at the equivalent recommended dosage of DANZITEN 142 mg twice daily treatment group. No patient had an absolute QTcF of greater than 500 msec while on study drug.
The most common hematologic adverse drug reactions (all Grades) were myelosuppression, including: thrombocytopenia (18%), neutropenia (15%), and anemia (8%). See Table 10 for Grade 3/4 laboratory abnormalities.
Discontinuation due to adverse reactions, regardless of relationship to study drug, was observed in 10% of patients.
In Adult Patients With Resistant or Intolerant Ph+ CML-CP and CML-AP
In the single-arm, open-label multicenter clinical trial, a total of 458 patients with Ph+ CML-CP and CML-AP resistant to or intolerant to at least one prior therapy, including imatinib were treated (CML-CP = 321; CML-AP = 137) at the equivalent recommended dosage of DANZITEN 190 mg twice daily.
The median duration of exposure in days for CML-CP and CML-AP patients is 561 (range, 1 to 1096) and 264 (range, 2 to 1160), respectively.
The median cumulative duration in days of dose interruptions for the CML-CP patients was 20 (range, 1 to 345), and the median duration in days of dose interruptions for the CML-AP patients was 23 (range, 1 to 234).
In patients with CML-CP, the most commonly reported non-hematologic adverse drug reactions (greater than or equal to 10%) were rash, pruritus, nausea, fatigue, headache, constipation, diarrhea, vomiting, and myalgia. The common serious drug-related adverse reactions (greater than or equal to 1% and less than 10%) were thrombocytopenia, neutropenia, and anemia.
In patients with CML-AP, the most commonly reported non-hematologic adverse drug reactions (greater than or equal to 10%) were rash, pruritus and fatigue. The common serious adverse drug reactions (greater than or equal to 1% and less than 10%) were thrombocytopenia, neutropenia, febrile neutropenia, pneumonia, leukopenia, intracranial hemorrhage, elevated lipase, and pyrexia.
Sudden deaths and QT prolongation were reported. The maximum mean QTcF change from baseline at steady- state was 10 msec. Increase in QTcF greater than 60 msec from baseline was observed in 4.1% of the patients and QTcF of greater than 500 msec was observed in 4 patients (less than 1%) [see Boxed Warning, Warnings and Precautions (5.3, 5.4), Clinical Pharmacology (12.2)].
Discontinuation due to adverse drug reactions was observed in 16% of CML-CP and 10% of CML-AP patients.
Most Frequently Reported Adverse Reactions
Tables 7 and 8 show the percentage of adult patients experiencing non-hematologic adverse reactions (excluding laboratory abnormalities) regardless of relationship to study drug. Adverse reactions reported in greater than 10% of adult patients who received at least 1 dose of Nilotinib are listed.
Table 7. Most Frequently Reported Non-Hematologic Adverse Reactions (Regardless of Relationship to Study Drug) in Adult Patients With Newly Diagnosed Ph+ CML-CP (≥ 10% in nilotinib 300 mg twice daily* or imatinib 400 mg once daily groups) 60-Month Analysisa

 |  | Patients With Newly Diagnosed Ph+ CML-CP
 |  | nilotinib 300 mg Twice Daily* | imatinib 400 mg Once Daily | nilotinib 300 mg Twice Daily* | imatinib 400 mg Once Daily
 |  | N = 279 | N = 280 | N = 279 | N = 280
Body System and Adverse Reaction |  | All Grades (%) |  | CTC Gradesb 3/4 (%)
Skin and subcutaneous tissue disorders | Rash | 38 | 19 | < 1 | 2
 | Pruritus | 21 | 7 | < 1 | 0
 | Alopecia | 13 | 7 | 0 | 0
 | Dry skin | 12 | 6 | 0 | 0
Gastrointestinal disorders | Nausea | 22 | 41 | 2 | 2
 | Constipation | 20 | 8 | < 1 | 0
 | Diarrhea | 19 | 46 | 1 | 4
 | Vomiting | 15 | 27 | < 1 | < 1
 | Abdominal pain upper | 18 | 14 | 1 | < 1
 | Abdominal pain | 15 | 12 | 2 | 0
 | Dyspepsia | 10 | 12 | 0 | 0
Nervous system disorders | Headache | 32 | 23 | 3 | < 1
 | Dizziness | 12 | 11 | < 1 | < 1
General disorders and administration-site conditions | Fatigue | 23 | 20 | 1 | 1
 | Pyrexia | 14 | 13 | < 1 | 0
 | Asthenia | 14 | 12 | < 1 | 0
 | Peripheral edema | 9 | 20 | < 1 | 0
 | Face edema | < 1 | 14 | 0 | < 1
Musculoskeletal and connective tissue disorders | Myalgia | 19 | 19 | < 1 | < 1
 | Arthralgia | 22 | 17 | < 1 | < 1
 | Muscle spasms | 12 | 34 | 0 | 1
 | Pain in extremity | 15 | 16 | < 1 | < 1
 | Back pain | 19 | 17 | 1 | 1
Respiratory, thoracic, and mediastinal disorders | Cough | 17 | 13 | 0 | 0
 | Oropharyngeal pain | 12 | 6 | 0 | 0
 | Dyspnea | 11 | 6 | 2 | < 1
Infections and infestations | Nasopharyngitis | 27 | 21 | 0 | 0
 | Upper respiratory tract infection | 17 | 14 | < 1 | 0
 | Influenza | 13 | 9 | 0 | 0
 | Gastroenteritis | 7 | 10 | 0 | < 1
Eye disorders | Eyelid edema | 1 | 19 | 0 | < 1
 | Periorbital edema | < 1 | 15 | 0 | 0
Psychiatric disorders | Insomnia | 11 | 9 | 0 | 0
Vascular disorder | Hypertension | 10 | 4 | 1 | < 1

Abbreviations: CML-CP, chronic myeloid leukemia-chronic phase; Ph+, Philadelphia chromosome positive.
aExcluding laboratory abnormalities.
bNCI Common Terminology Criteria (CTC) for Adverse Events, version 3.0.
*Equivalent to the recommended dosage of DANZITEN 142 mg twice daily.

Table 8. Most Frequently Reported Non-Hematologic Adverse Reactions in Adult Patients with Resistant or Intolerant Ph+ CML Receiving Nilotinib 400 mg Twice Daily* (regardless of relationship to study drug) (≥ 10% in any group) 24-Month Analysisa

Body System and Adverse Reaction |  | CML-CP |  | CML-AP
Body System and Adverse Reaction |  | N = 321 |  | N = 137
Body System and Adverse Reaction |  | All Grades (%) | CTC Gradesb 3/4 (%) | All Grades (%) | CTC Gradesb 3/4 (%)
Skin and subcutaneous tissue disorders | Rash | 36 | 2 | 29 | 0
 | Pruritus | 32 | < 1 | 20 | 0
 | Night sweat | 12 | < 1 | 27 | 0
 | Alopecia | 11 | 0 | 12 | 0
Gastrointestinal disorders | Nausea | 37 | 1 | 22 | < 1
 | Constipation | 26 | < 1 | 19 | 0
 | Diarrhea | 28 | 3 | 24 | 2
 | Vomiting | 29 | < 1 | 13 | 0
 | Abdominal pain | 15 | 2 | 16 | 3
 | Abdominal pain upper | 14 | < 1 | 12 | < 1
 | Dyspepsia | 10 | < 1 | 4 | 0
Nervous system disorders | Headache | 35 | 2 | 20 | 1
General disorders and administration-site conditions | Fatigue | 32 | 3 | 23 | < 1
 | Pyrexia | 22 | < 1 | 28 | 2
 | Asthenia | 16 | 0 | 14 | 1
 | Peripheral edema | 15 | < 1 | 12 | 0
Musculoskeletal and connective tissue disorders | Myalgia | 19 | 2 | 16 | < 1
 | Arthralgia | 26 | 2 | 16 | 0
 | Muscle spasms | 13 | < 1 | 15 | 0
 | Bone pain | 14 | < 1 | 15 | 2
 | Pain in extremity | 20 | 2 | 18 | 1
 | Back pain | 17 | 2 | 15 | < 1
 | Musculoskeletal pain | 11 | < 1 | 12 | 1
Respiratory, thoracic, and mediastinal disorders | Cough | 27 | < 1 | 18 | 0
 | Dyspnea | 15 | 2 | 9 | 2
 | Oropharyngeal pain | 11 | 0 | 7 | 0
Infections and infestations | Nasopharyngitis | 24 | < 1 | 15 | 0
 | Upper respiratory tract infection | 12 | 0 | 10 | 0
Metabolism and nutrition disorders | Decreased appetitec | 15 | < 1 | 17 | < 1
Psychiatric disorders | Insomnia | 12 | 1 | 7 | 0
Vascular disorders | Hypertension | 10 | 2 | 11 | < 1

Abbreviations: CML-AP, chronic myeloid leukemia-accelerated phase; CML-CP, chronic myeloid leukemia-chronic phase; Ph+, Philadelphia chromosome positive.
aExcluding laboratory abnormalities.
bNCI Common Terminology Criteria for Adverse Events, version 3.0.
cAlso includes preferred term anorexia.
*Equivalent to the recommended dosage of DANZITEN 190 mg twice daily.

Laboratory Abnormalities

Table 9 shows the percentage of adult patients experiencing treatment-emergent Grade 3/4 laboratory abnormalities in patients who received at least one dose of nilotinib.

Table 9. Percent Incidence of Clinically Relevant Grade 3/4* Laboratory Abnormalities

 | Patient Population
 | Newly Diagnosed Adult Ph+ CML-CP |  | Resistant or Intolerant Adult Ph+
 | Newly Diagnosed Adult Ph+ CML-CP |  | CML-CP | CML-AP
 | nilotinib 300 mga | imatinib 400 mg | nilotinib 400 mgb | nilotinib 400 mgb
 | Twice Daily | Once Daily | Twice Daily | Twice Daily
 | N = 279 | N = 280 | N = 321 | N = 137
 | (%) | (%) | (%) | (%)
Hematologic Parameters
Thrombocytopenia | 10 | 9 | 30^1 | 42^3
Neutropenia | 12 | 22 | 31^2 | 42^4
Anemia | 4 | 6 | 11 | 27
Biochemistry Parameters
Elevated lipase | 9 | 4 | 18 | 18
Hyperglycemia | 7 | < 1 | 12 | 6
Hypophosphatemia | 8 | 10 | 17 | 15
Elevated bilirubin (total) | 4 | < 1 | 7 | 9
Elevated SGPT (ALT) | 4 | 3 | 4 | 4
Hyperkalemia | 2 | 1 | 6 | 4
Hyponatremia | 1 | < 1 | 7 | 7
Hypokalemia | < 1 | 2 | 2 | 9
Elevated SGOT (AST) | 1 | 1 | 3 | 2
Decreased albumin | 0 | < 1 | 4 | 3
Hypocalcemia | < 1 | < 1 | 2 | 5
Elevated alkaline phosphatase | 0 | < 1 | < 1 | 1
Elevated creatinine | 0 | < 1 | < 1 | < 1

Abbreviations: ALT alanine aminotransferase; AST, aspartate aminotransferase; CML-AP, chronic myeloid leukemia-accelerated phase; CML-CP, chronic myeloid leukemia-chronic phase; Ph+, Philadelphia chromosome positive.
*NCI Common Terminology Criteria for Adverse Events, version 3.0.
^1CML-CP: Thrombocytopenia: 12% were Grade 3, 18% were Grade 4.
^2CML-CP: Neutropenia: 16% were Grade 3, 15% were Grade 4.
^3CML-AP: Thrombocytopenia: 11% were Grade 3, 32% were Grade 4.
^4CML-AP: Neutropenia: 16% were Grade 3, 26% were Grade 4.
a Equivalent to the recommended dosage of DANZITEN 142 mg twice daily.
b Equivalent to the recommended dosage of DANZITEN 190 mg twice daily.

Elevated total cholesterol (all Grades) occurred in 28% (equivalent recommended dosage of DANZITEN 142 mg twice daily) and 4% (imatinib). Elevated triglycerides (all Grades) occurred in 12% and 8% of patients in the nilotinib and imatinib arms, respectively. Hyperglycemia (all Grades) occurred in 50% and 31% of patients in the nilotinib and imatinib arms, respectively.
Most common biochemistry laboratory abnormalities (all Grades) were alanine aminotransferase increased (72%), blood bilirubin increased (59%), aspartate aminotransferase increased (47%), lipase increased (28%), blood glucose increased (50%), blood cholesterol increased (28%), and blood triglyceride increased (12%).
Treatment Discontinuation in Patients With Ph+ CML-CP Who Have Achieved a Sustained Molecular Response (MR4.5)
In eligible patients who discontinued nilotinib therapy after attaining a sustained molecular response (MR4.5), musculoskeletal symptoms (e.g., myalgia, pain in extremity, arthralgia, bone pain, spinal pain, or musculoskeletal pain), were reported more frequently than before treatment discontinuation in the first year, as noted in Table 9. The rate of new musculoskeletal symptoms generally decreased in the second year after treatment discontinuation.
In the newly diagnosed population in whom musculoskeletal symptoms occurred at any time during the TFR phase, 23/53 (43%) had not resolved by the TFR end date or data cut-off date. In the population previously treated with imatinib in whom musculoskeletal events occurred at any time during the TFR phase, 32/57 (56%) had not resolved by the data cut-off date.
The rate of musculoskeletal symptoms decreased in patients who entered the nilotinib treatment reinitiation (NTRI) phase, at 11/88 (13%) in the newly diagnosed population and 14/56 (25%) in the population previously treated with imatinib. Other adverse reactions observed in the nilotinib re-treatment phase were similar to those observed during nilotinib use in patients with newly diagnosed Ph+ CML-CP and resistant or intolerant Ph+ CML-CP and CML-AP.

Table 10. Musculoskeletal Symptoms Occurring Upon Treatment Discontinuation in the Context of Treatment-Free Remission (TFR)

 | Entire TFR Period in all TFR Patients |  |  |  | By Time Interval, in Subset of Patients in TFR Greater than 48 Weeks
Ph+ CML- CP patients | N | Median follow- up in | Patients with musculoskeletal symptoms |  | N | Year prior to nilotinib discontinuation |  | 1st year after nilotinib discontinuation |  | 2nd year after nilotinib discontinuation
Ph+ CML- CP patients | N | TFR | All Grades | Grade 3/4 | N | All Grades | Grade 3/4 | All Grades | Grade 3/4 | All Grades | Grade 3/4
Newly Diagnosed | 190 | 76 weeks | 28% | 1% | 100 | 17% | 0% | 34% | 2% | 9% | 0%
Previously treated with imatinib | 126 | 99 weeks | 45% | 2% | 73 | 14% | 0% | 48% | 3% | 15% | 1%

Abbreviations: CML-CP, chronic myeloid leukemia-chronic phase; Ph+, Philadelphia chromosome positive ;TFR, treatment-free remission.

Additional Data from Clinical Trials
The following adverse drug reactions were reported in adult patients in the nilotinib clinical studies at the recommended doses. These adverse drug reactions are ranked under a heading of frequency, the most frequent first using the following convention: common (greater than or equal to 1% and less than 10%), uncommon (greater than or equal to 0.1% and less than 1%), and unknown frequency (single events). For laboratory abnormalities, very common events (greater than or equal to 10%), which were not included in Tables 7 and 8, are also reported. These adverse reactions are included based on clinical relevance and ranked in order of decreasing seriousness within each category, obtained from 2 clinical studies:
1. Adult patients with newly diagnosed Ph+ CML-CP 60 month analysis and,
2. Adult patients with resistant or intolerant Ph+ CML-CP and CMP-AP 24 months’ analysis.

Infections and Infestations: Common: folliculitis. Uncommon: pneumonia, bronchitis, urinary tract infection, candidiasis (including oral candidiasis). Unknown frequency: hepatitis B reactivation, sepsis, subcutaneous abscess, anal abscess, furuncle, tinea pedis.

Neoplasms Benign, Malignant, and Unspecified: Common: skin papilloma. Unknown frequency: oral papilloma, paraproteinemia.
Blood and Lymphatic System Disorders: Common: leukopenia, eosinophilia, febrile neutropenia, pancytopenia, lymphopenia. Unknown frequency: thrombocythemia, leukocytosis.

Immune System Disorders: Unknown frequency: hypersensitivity.

Endocrine Disorders: Uncommon: hyperthyroidism, hypothyroidism. Unknown frequency: hyperparathyroidism secondary, thyroiditis.

Metabolism and Nutrition Disorders: Very Common: hypophosphatemia. Common: electrolyte imbalance (including hypomagnesemia, hyperkalemia, hypokalemia, hyponatremia, hypocalcemia, hypercalcemia, hyperphosphatemia), diabetes mellitus, hyperglycemia, hypercholesterolemia, hyperlipidemia, hypertriglyceridemia. Uncommon: gout, dehydration, increased appetite. Unknown frequency: hyperuricemia, hypoglycemia.

Psychiatric Disorders: Common: depression, anxiety. Unknown frequency: disorientation, confusional state, amnesia, dysphoria.

Nervous System Disorders: Common: peripheral neuropathy, hypoesthesia, paresthesia. Uncommon: intracranial hemorrhage, ischemic stroke, transient ischemic attack, cerebral infarction, migraine, loss of consciousness (including syncope), tremor, disturbance in attention, hyperesthesia, facial paralysis. Unknown frequency: basilar artery stenosis, brain edema, optic neuritis, lethargy, dysesthesia, restless legs syndrome.

Eye Disorders: Common: eye hemorrhage, eye pruritus, conjunctivitis, dry eye (including xerophthalmia). Uncommon: vision impairment, vision blurred, visual acuity reduced, photopsia, hyperemia (scleral, conjunctival, ocular), eye irritation, conjunctival hemorrhage. Unknown frequency: papilledema, diplopia, photophobia, eye swelling, blepharitis, eye pain, chorioretinopathy, conjunctivitis allergic, ocular surface disease.

Ear and Labyrinth Disorders: Common: vertigo. Unknown frequency: hearing impaired, ear pain, tinnitus.

Cardiac Disorders: Common: angina pectoris, arrhythmia (including atrioventricular block, cardiac flutter, extrasystoles, atrial fibrillation, tachycardia, bradycardia), palpitations, electrocardiogram QT prolonged.
Uncommon: cardiac failure, myocardial infarction, coronary artery disease, cardiac murmur, coronary artery stenosis, myocardial ischemia, pericardial effusion, cyanosis. Unknown frequency: ventricular dysfunction, pericarditis, ejection fraction decrease.

Vascular Disorders: Common: flushing. Uncommon: hypertensive crisis, peripheral arterial occlusive disease, intermittent claudication, arterial stenosis limb, hematoma, arteriosclerosis. Unknown frequency: shock hemorrhagic, hypotension, thrombosis, peripheral artery stenosis.

Respiratory, Thoracic and Mediastinal Disorders: Common: dyspnea exertional, epistaxis, dysphonia. Uncommon: pulmonary edema, pleural effusion, interstitial lung disease, pleuritic pain, pleurisy, pharyngolaryngeal pain, throat irritation. Unknown frequency: pulmonary hypertension, wheezing.

Gastrointestinal Disorders: Common: pancreatitis, abdominal discomfort, abdominal distension, dysgeusia, flatulence. Uncommon: gastrointestinal hemorrhage, melena, mouth ulceration, gastroesophageal reflux, stomatitis, esophageal pain, dry mouth, gastritis, sensitivity of teeth. Unknown frequency: gastrointestinal ulcer perforation, retroperitoneal hemorrhage, hematemesis, gastric ulcer, esophagitis ulcerative, subileus, enterocolitis, hemorrhoids, hiatus hernia, rectal hemorrhage, gingivitis.

Hepatobiliary Disorders: Very common: hyperbilirubinemia. Common: hepatic function abnormal. Uncommon: hepatotoxicity, toxic hepatitis, jaundice. Unknown frequency: cholestasis, hepatomegaly.

Skin and Subcutaneous Tissue Disorders: Common: eczema, urticaria, erythema, hyperhidrosis, contusion, acne, dermatitis (including allergic, exfoliative and acneiform). Uncommon: exfoliative rash, drug eruption, pain of skin, ecchymosis. Unknown frequency: psoriasis, erythema multiforme, erythema nodosum, skin ulcer, palmar-plantar erythrodysesthesia syndrome, petechiae, photosensitivity, blister, dermal cyst, sebaceous hyperplasia, skin atrophy, skin discoloration, skin exfoliation, skin hyperpigmentation, skin hypertrophy, hyperkeratosis.

Musculoskeletal and Connective Tissue Disorders: Common: bone pain, musculoskeletal chest pain, musculoskeletal pain, back pain, neck pain, flank pain, muscular weakness. Uncommon: musculoskeletal stiffness, joint swelling. Unknown frequency: arthritis.

Renal and Urinary Disorders: Common: pollakiuria. Uncommon: dysuria, micturition urgency, nocturia. Unknown frequency: renal failure, hematuria, urinary incontinence, chromaturia.

Reproductive System and Breast Disorders: Uncommon: breast pain, gynecomastia, erectile dysfunction. Unknown frequency: breast induration, menorrhagia, nipple swelling.

General Disorders and Administration Site Conditions: Common: pyrexia, chest pain (including non-cardiac chest pain), pain, chest discomfort, malaise. Uncommon: gravitational edema, influenza-like illness, chills, feeling body temperature change (including feeling hot, feeling cold). Unknown frequency: localized edema.

Investigations: Very Common: alanine aminotransferase increased, aspartate aminotransferase increased, lipase increased, lipoprotein cholesterol (including very low density and high density) increased, total cholesterol increased, blood triglycerides increased. Common: hemoglobin decreased, blood amylase increased, gamma- glutamyltransferase increased, blood creatinine phosphokinase increased, blood alkaline phosphatase increased, weight decreased, weight increased, globulins decreased. Uncommon: blood lactate dehydrogenase increased, blood urea increased. Unknown frequency: troponin increased, blood bilirubin unconjugated increased, insulin C-peptide decreased, blood parathyroid hormone increased.

In Pediatric Patients With Newly Diagnosed Ph+ CML-CP or Resistant or Intolerant Ph+ CML-CP
In pediatric patients with Ph+ CML-CP, the most common (greater than 20%) non-hematologic adverse reactions were hyperbilirubinemia, headache, alanine aminotransferase increased, rash, pyrexia, nausea, aspartate aminotransferase increased, pain in extremity, upper respiratory tract infection, vomiting, diarrhea, and nasopharyngitis. The most common (greater than 5%) Grade 3/4 non-hematologic adverse reactions were hyperbilirubinemia, rash, alanine aminotransferase increased, and neutropenia.
Laboratory abnormalities of hyperbilirubinemia (Grade 3/4: 16%) and transaminase elevation (AST Grade 3/4: 2.9%, ALT Grade 3/4: 10%), were reported at a higher frequency than in adult patients.
The most common hematological laboratory abnormalities (greater than or equal to 30% of patients, of all Grades) were decreases in total white blood cells (54%), platelet count (44%), absolute neutrophils (44%), hemoglobin (38%), and absolute lymphocytes (36%).
Discontinuation of study treatment due to adverse reactions occurred in 15 patients (22%). The most frequent adverse reactions leading to discontinuation were hyperbilirubinemia (9%) and rash (6%).
Increase in QTcF greater than 30 msec from baseline was observed in 19 patients (28%). No patient had an absolute QTcF of greater than 500 msec or QTcF increase of greater than 60 msec from baseline.

Growth Retardation in Pediatric Population
Close monitoring of growth in pediatric patients under nilotinib treatment is recommended [see Warnings and Precautions (5.14)].

Additional pediatric use information is approved for Novartis Pharmaceuticals Corporation’s Tasigna® (nilotinib) capsules. However, due to Novartis Pharmaceuticals Corporation’s marketing exclusivity rights, this drug product is not labeled with that pediatric information.

6.2 Postmarketing Experience

The following adverse reactions have been identified during postapproval use of nilotinib. Because these reactions are reported voluntarily from a population of uncertain size, it is not always possible to reliably estimate their frequency or establish a causal relationship to drug exposure.
Blood and Lymphatic System Disorders: thrombotic microangiopathy
Nervous System Disorders: facial paralysis

Musculoskeletal and Connective Tissue Disorders: osteonecrosis

7 DRUG INTERACTIONS

7.1 Effect of Other Drugs on DANZITEN

Strong CYP3A Inhibitors
Avoid concomitant use of strong CYP3A inhibitors with DANZITEN. If concomitant use cannot be avoided, reduce DANZITEN dose [see Dosage and Administration (2.9)].
Nilotinib is a CYP3A substrate [see Clinical Pharmacology (12.3)]. Concomitant use with a strong CYP3A inhibitor increases nilotinib exposure [see Clinical Pharmacology (12.3)], which may increase the risk of DANZITEN adverse reactions.
Strong CYP3A Inducers
Avoid concomitant use of strong CYP3A inducers with DANZITEN.
Nilotinib is a CYP3A substrate [see Clinical Pharmacology (12.3)]. Concomitant use with a strong CYP3A inducer decreases nilotinib exposure [see Clinical Pharmacology (12.3)], which may reduce DANZITEN efficacy.
Proton Pump Inhibitors
Avoid concomitant use of PPI with DANZITEN. As an alternative to PPIs, use H2 blockers approximately 10 hours before or approximately 2 hours after the dose of DANZITEN, or use antacids approximately 2 hours before or approximately 2 hours after the dose of DANZITEN.
Nilotinib displays pH-dependent aqueous solubility [see Description (11)]. Concomitant use with a proton pump inhibitor (PPI) decreases nilotinib concentrations [see Clinical Pharmacology (12.3)], which may reduce DANZITEN efficacy.

7.2 Drugs that Prolong the QT Interval

Avoid coadministration of DANZITEN with agents that may prolong the QT interval, such as anti-arrhythmic drugs [see Boxed Warning, Dosage and Administration (2.5), Warnings and Precautions (5.3), Drug Interactions (7.1), Clinical Pharmacology (12.2)].
Nilotinib is associated with a clinically significant concentration-dependent QT prolongation [see Clinical Pharmacology (12.2)].

8 USE IN SPECIFIC POPULATIONS

8.1 Pregnancy

Risk Summary
Based on findings from animal studies and the mechanism of action, DANZITEN can cause fetal harm when administered to a pregnant woman [see Clinical Pharmacology (12.1)]. There are no available data in pregnant women to inform the drug-associated risk. In animal reproduction studies, administration of nilotinib to pregnant rats and rabbits during organogenesis caused adverse developmental outcomes, including embryo-fetal lethality, fetal effects, and fetal variations in rats and rabbits at maternal exposures (AUC) approximately 2 and 0.5 times, respectively, the exposures in patients at the recommended dose (see Data). Advise pregnant women of the potential risk to a fetus.
The background risk of major birth defects and miscarriage for the indicated population is unknown. All pregnancies have a background risk of birth defect, loss, or other adverse outcomes. In the U.S. general population, the estimated background risk of major birth defects and miscarriage in clinically recognized pregnancies are 2%-4% and 15%-20%, respectively.
Data
Animal Data
In embryo-fetal development studies in rats and rabbits, pregnant animals received oral doses of nilotinib up to 100 mg/kg/day and 300 mg/kg/day, respectively, during the period of organogenesis.
In rats, oral administration of nilotinib produced embryo-lethality/fetal effects at doses ≥ 30 mg/kg/day. At ≥ 30 mg/kg/day, skeletal variations of incomplete ossification of the frontals and misshapen sternebra were noted, and there was an increased incidence of small renal papilla and fetal edema. At 100 mg/kg/day, nilotinib was associated with maternal toxicity (decreased gestation weight, gravid uterine weight, net weight gain, and food consumption) and resulted in a single incidence of cleft palate and two incidences of pale skin were noted in the fetuses. A single incidence of dilated ureters was noted in a fetus also displaying small renal papilla at 100 mg/kg/day. Additional variations of forepaw and hindpaw phalanx unossified, fused sternebra, bipartite sternebra ossification, and incomplete ossification of the cervical vertebra were noted at 100 mg/kg/day.
In rabbits, oral administration of nilotinib resulted in the early sacrifice of two females, maternal toxicity and increased resorption of fetuses at 300 mg/kg/day. Fetal skeletal variations (incomplete ossification of the hyoid, bent hyoid, supernumerary short detached ribs and the presence of additional ossification sites near the nasals, frontals and in the sternebral column) were also increased at this dose in the presence of maternal toxicity.
Slight maternal toxicity was evident at 100 mg/kg/day but there were no reproductive or embryo-fetal effects at this dose.
At 30 mg/kg/day in rats and 300 mg/kg/day in rabbits, the maternal systemic exposure (AUC) were 72700 ng*hr/mL and 17100 ng*hr/mL respectively, representing approximately 2 and 0.5 times the exposure in humans at the highest recommended dose 400 mg twice daily.
When pregnant rats were dosed with nilotinib during organogenesis and through lactation, the adverse effects included a longer gestational period, lower pup body weights until weaning and decreased fertility indices in the pups when they reached maturity, all at a maternal dose of 60 mg/kg (i.e., 360 mg/m2, approximately 0.7 times the clinical dose of 400 mg twice daily based on body surface area). At doses up to 20 mg/kg (i.e., 120 mg/m2, approximately 0.25 times the clinical dose of 400 mg twice daily based on body surface area) no adverse effects were seen in the maternal animals or the pups.

8.2 Lactation

Risk Summary
There are no data on the presence of nilotinib or its metabolites in human milk or its effects on a breastfed child or on milk production. However, nilotinib is present in the milk of lactating rats. Because of the potential for serious adverse reactions in a breastfed child, advise women not to breastfeed during treatment with DANZITEN and for 14 days after the last dose.
Animal Data
After a single 20 mg/kg of [14C] nilotinib dose to lactating rats, the transfer of parent drug and its metabolites into milk was observed. The overall milk-to-plasma exposure ratio of total radioactivity was approximately 2, based on the AUC0-24h or AUC0-INF values. No rat metabolites of nilotinib were detected that were unique to milk.

8.3 Females and Males of Reproductive Potential

Based on animal studies, DANZITEN can cause fetal harm when administered to a pregnant woman [see Use in Specific Populations (8.1)].
Pregnancy Testing
Females of reproductive potential should have a pregnancy test prior to starting treatment with DANZITEN.

Contraception
Females
Advise females of reproductive potential to use effective contraception during treatment with DANZITEN and for 14 days after the last dose.
Infertility
The risk of infertility in females or males of reproductive potential has not been studied in humans. In studies in rats and rabbits, the fertility in males and females was not affected [see Nonclinical Toxicology (13.1)].

8.4 Pediatric Use

The frequency, type, and severity of adverse reactions observed were generally consistent with those observed in adults, with the exception of the laboratory abnormalities of hyperbilirubinemia (Grade 3/4: 16%) and transaminase elevation (AST Grade 3/4: 2.9%, ALT Grade 3/4: 10%), which were reported at a higher frequency in pediatric patients than in adults [see Adverse Reactions (6.1)]. For pediatric growth and development, growth retardation has been reported in pediatric patients with Ph+ CML-CP treated with nilotinib [see Warnings and Precautions (5.14 and 5.12), Adverse Reactions (6.1)].
The safety and effectiveness of nilotinib in pediatric patients below the age of 1 year with newly diagnosed, or resistant or intolerant Ph+ CML in chronic phase and accelerated phase, have not been established.

Additional pediatric use information is approved for Novartis Pharmaceuticals Corporation’s Tasigna® (nilotinib) capsules. However, due to Novartis Pharmaceuticals Corporation’s marketing exclusivity rights, this drug product is not labeled with that pediatric information.

8.5 Geriatric Use

In the clinical trials of nilotinib (patients with newly diagnosed Ph+ CML-CP and resistant or intolerant Ph+ CML-CP and CML-AP), approximately 12% and 30% of patients were 65 years or over respectively.
• Patients with newly diagnosed Ph+ CML-CP: There was no difference in major molecular response between patients aged less than 65 years and those greater than or equal to 65 years.
• Patients with resistant or intolerant CML-CP: There was no difference in major cytogenetic response rate between patients aged less than 65 years and those greater than or equal to 65 years.
• Patients with resistant or intolerant CML-AP: The hematologic response rate was 44% in patients less than 65 years of age and 29% in patients greater than or equal to 65 years.
No major differences for safety were observed in patients greater than or equal to 65 years of age as compared to patients less than 65 years.

8.6 Cardiac Disorders

In the clinical trials, patients with a history of uncontrolled or significant cardiovascular disease, including recent myocardial infarction, congestive heart failure, unstable angina or clinically significant bradycardia, were excluded. Caution should be exercised in patients with relevant cardiac disorders [see Boxed Warning, Warnings and Precautions (5.3)].

8.7 Hepatic Impairment

Reduce the DANZITEN dosage in patients with hepatic impairment and monitor the QT interval closely [see Dosage and Administration (2.8), Clinical Pharmacology (12.3)].

10 OVERDOSAGE

Overdose with nilotinib has been reported, where an unspecified number of nilotinib were ingested in combination with alcohol and other drugs. Events included neutropenia, vomiting, and drowsiness. In the event of overdose, observe the patient and provide appropriate supportive treatment.

11 DESCRIPTION

DANZITEN (nilotinib) tablets contain nilotinib, a kinase inhibitor.
Nilotinib is present as nilotinib tartrate, with the molecular formula of C28H22F3N7O . C4H6O6 and a weight of 679.61 g/mol. Nilotinib tartrate is a white to slightly yellowish powder. The solubility of nilotinib tartrate in aqueous solutions decreases with increasing pH. The pKa1 was determined to be 3.53; pKa2 was estimated to be 1.55.
The chemical name of nilotinib tartrate is 4-methyl-N-[3-(4-methyl-1H-imidazol-1-yl)-5-(trifluoromethyl)phenyl]-3-[[4-(3-pyridinyl)-2-pyrimidinyl]amino]benzamide,(2R,3R)-2,3-dihydroxybutanedionate. Its structure is shown below:

DANZITEN (nilotinib) tablets contain 71 mg or 95 mg nilotinib, equivalent to 91.14 mg, and 121.95 mg nilotinib tartrate, respectively. The inactive ingredients are: colloidal silicon dioxide, croscarmellose sodium, hypromellose acetate succinate, iron oxide red (in 71 mg strength tablets), iron oxide yellow (in 95 mg strength tablets), magnesium stearate, microcrystalline cellulose, polyethylene glycol, polyvinyl alcohol, talc, and titanium dioxide.

12 CLINICAL PHARMACOLOGY

12.1 Mechanism of Action

Nilotinib is an inhibitor of the BCR-ABL kinase. Nilotinib binds to and stabilizes the inactive conformation of the kinase domain of ABL protein. In vitro, nilotinib inhibited BCR-ABL mediated proliferation of murine leukemic cell lines and human cell lines derived from patients with Ph+ CML. Under the conditions of the assays, nilotinib was able to overcome imatinib resistance resulting from BCR-ABL kinase mutations, in 32 out of 33 mutations tested. Nilotinib inhibited the autophosphorylation of the following kinases at IC50 values as indicated: BCR-ABL (20 to 60 nM), PDGFR (69 nM), c-KIT (210 nM), CSF-1R (125 to 250 nM), and DDR1 (3.7 nM).

12.2 Pharmacodynamics

A relationship between nilotinib exposure and a greater likelihood of response and safety events, including a higher occurrence of total bilirubin elevations, was observed in clinical studies.
Nilotinib time course of pharmacodynamic response is unknown.
Cardiac Electrophysiology
Nilotinib is associated with concentration-dependent QT prolongation. At the equivalent recommended dosage of DANZITEN 190 mg twice daily given without food in healthy subjects, the maximum mean placebo-adjusted QTcF changes were 10.4 msec (90% CI: 2.85, 18.0). After a single equivalent recommended dose of DANZITEN 380 mg (two times the maximum approved recommended dose) given with a high fat meal to healthy subjects, the maximum mean placebo-adjusted QTcF changes were) 18.0 msec (90% CI: 9.65, 25.8). Peak plasma concentrations in the QT study were 26% lower than or comparable with those observed in patients enrolled in the single-arm study [see Boxed Warning, Warnings and Precautions (5.3), Adverse Reactions (6.1)]. No new significant QT findings were observed in healthy subject studies with single doses of DANZITEN given with or without food. Throughout the 14 PK studies there were no QT prolongation events associated with DANZITEN.

12.3 Pharmacokinetics

Nilotinib single-dose maximum concentration (Cmax), area under the time concentration curve (AUC), predicted steady-state maximum concentration (Cmax,ss) and area under the time concentration curve (AUCss) in fasted subjects receiving the DANZITEN approved recommended dosages are presented in Tables 11 and 12.

Table 11: Nilotinib mean ±SD single-dose exposure in fasted patients receiving the DANZITEN approved recommended dosages

DANZITEN Dosage | Cmax | AUC
142 mg | 849 ± 366 ng/mL | 17637 ± 7744 ng*hr/mL
190 mg | 811 ± 300 ng/mL | 15339 ± 6935 ng*hr/mL
Abbreviations: Cmax= maximum concentration; AUC = area under the time concentration curve

Table 12: Nilotinib predicted mean ±SD steady-state exposure in fasted patients receiving the DANZITEN approved recommended dosages

DANZITEN Dosage | Cmax,ss | AUCss
142 mg twice daily | 2071 ± 761 ng/mL | 14525 ± 5690 ng*hr/mL
190 mg twice daily | 2229 ± 790 ng/mL | 15662 ± 5738 ng*hr/mL
Abbreviations: Cmax,ss= maximum concentration; AUCss = area under the time concentration curve at steady state

Absorption
The median time (range) to reach peak plasma nilotinib concentrations (Tmax) is 2.7 (1.0 to 4.7 hours) following single dose administration of DANZITEN 190 mg in fasted healthy subjects.
Effect of Food
No clinically significant differences in nilotinib exposure were observed following administration of DANZITEN 142 mg or 190 mg with a high-fat meal (800 to 1000 calories, 50% fat) or a low-fat meal (400-500 kcal, 25% fat content) compared to fasted healthy subjects.
Distribution
Serum protein binding is approximately 98% with a blood-to-serum ratio of 0.68.
Elimination
The mean elimination half-life of nilotinib is approximately 14 hours.
Metabolism
Nilotinib is primarily metabolized via CYP3A4-mediated oxidation and to a minor extent by CYP2C8.
Excretion
After a single dose of radiolabeled nilotinib, more than 90% of the administered dose was eliminated within
7 days: 93% of the dose in feces. Parent drug accounted for 69% of the dose.
Specific Populations
No clinically significant differences in the pharmacokinetic of nilotinib were observed based on age, sex, race/ethnicity, or body weight. The effect of renal impairment on nilotinib pharmacokinetics is unknown.

Additional pediatric use information is approved for Novartis Pharmaceuticals Corporation’s Tasigna® (nilotinib) capsules. However due to Novartis Pharmaceuticals Corporation’s marketing exclusivity rights, this drug product is not labeled with that pediatric information.

Patients with Hepatic Impairment
Nilotinib mean AUC increased 1.4-fold in mild (Child-Pugh class A), 1.4-fold in moderate (Child-Pugh class B), and 1.6-fold in severe (Child-Pugh class C) hepatic impairment subjects following a single equivalent recommended dose of DANZITEN 95 mg (66% of the lowest approved recommended dosage).
Drug Interaction Studies
Clinical Studies
Strong CYP3A Inhibitors: Nilotinib AUC increased by approximately 3-fold following concomitant administration of ketoconazole (strong CYP3A inhibitor) 400 mg once daily for 6 days. Nilotinib AUC increased by 1.3-fold with concomitant use with double-strength grapefruit juice.
Strong CYP3A Inducers: Nilotinib AUC decreased by approximately 80% following concomitant use with rifampicin (strong CYP3A inducer) 600 mg daily.
Proton Pump Inhibitors (PPIs): Nilotinib displays pH-dependent aqueous solubility [see Description (11)]. Nilotinib AUC decreased by 34% following concomitant use of multiple doses of esomeprazole (PPI) 40 mg daily.
Other Drugs: No clinically significant differences in nilotinib pharmacokinetics were observed when used concomitantly with imatinib (moderate CYP3A inhibitor), famotidine (an H2 blocker), or an antacid. No clinically significant differences in the pharmacokinetics of the following drugs were observed when used concomitantly with nilotinib; oral midazolam (CYP3A substrate), imatinib, or warfarin (CYP2C9 substrate).
In Vitro Studies Where Drug Interaction Potential was not Further Evaluated Clinically
CYP Enzymes: Nilotinib is a competitive inhibitor of CYP2C8, CYP2D6, and is an inducer of CYP2B6 and CYP2C8.
Transporter Systems: Nilotinib is an inhibitor of UGT1A1 and P-gp.

12.5 Pharmacogenomics

Nilotinib can increase bilirubin levels. The (TA)7/(TA)7 genotype of UGT1A1 was associated with a statistically significant increase in the risk of hyperbilirubinemia relative to the (TA)6/(TA)6 and (TA)6/(TA)7 genotypes. However, the largest increases in bilirubin were observed in the (TA)7/(TA)7 genotype (UGT1A1*28) patients [see Warnings and Precautions (5.7)].

13 NONCLINICAL TOXICOLOGY

13.1 Carcinogenesis, Mutagenesis, Impairment of Fertility

A 2-year carcinogenicity study was conducted orally in rats at nilotinib doses of 5, 15, and 40 mg/kg/day. Exposures in animals at the highest dose tested were approximately 2- to 3-fold the human exposure (based on AUC) at the nilotinib dose of 400 mg twice daily. The study was negative for carcinogenic findings. A 26-week carcinogenicity study was conducted orally in Tg.rasH2 mice, a model genetically modified to enhance susceptibility to neoplastic transformation, at nilotinib doses of 30, 100, and 300 mg/kg/day. Nilotinib induced in the skin and subcutis statistically significant increases in the incidence of papillomas in females and of papillomas and combined papillomas and carcinomas in males at 300 mg/kg/day. The no-observed-adverse- effect-level (NOAEL) for skin neoplastic lesions was 100 mg/kg/day.
Nilotinib was not mutagenic in a bacterial mutagenesis (Ames) assay, was not clastogenic in a chromosome aberration assay in human lymphocytes, did not induce DNA damage (comet assay) in L5178Y mouse lymphoma cells, nor was it clastogenic in an in vivo rat bone marrow micronucleus assay with two oral treatments at doses up to 2000 mg/kg/dose.
There were no effects on male or female rat and female rabbit mating or fertility at doses up to 180 mg/kg in rats (approximately 4- to 7-fold for males and females, respectively, the AUC in patients at the dose of 400 mg twice daily) or 300 mg/kg in rabbits (approximately one-half the AUC in patients at the dose of 400 mg twice daily). The effect of nilotinib on human fertility is unknown. In a study where male and female rats were treated with nilotinib at oral doses of 20 to 180 mg/kg/day (approximately 1- to 6.6-fold the AUC in patients at the dose of 400 mg twice daily) during the pre-mating and mating periods and then mated, and dosing of pregnant rats continued through gestation Day 6, nilotinib increased post-implantation loss and early resorption, and decreased the number of viable fetuses and litter size at all doses tested.

14 CLINICAL STUDIES

14.1 Adult Newly Diagnosed Ph+ CML-CP

The effectiveness of 142 mg twice daily of DANZITEN (nilotinib) tablets for the treatment of adult patients with newly diagnosed Ph+ CML-CP has been established from an adequate and well-controlled study of Tasigna® (nilotinib) capsules, which has a different recommended dosage than DANZITEN. Below is a display of the results of Tasigna® (nilotinib) capsules in this adequate and well-controlled study.
The ENESTnd (Evaluating Nilotinib Efficacy and Safety in clinical Trials-Newly Diagnosed patients) study (NCT00471497) was an open-label, multicenter, randomized trial conducted to determine the efficacy of nilotinib versus imatinib in adult patients with cytogenetically confirmed newly diagnosed Ph+ CML-CP. Patients were within 6 months of diagnosis and were previously untreated for CML-CP, except hydroxyurea and/or anagrelide. Efficacy was based on a total of 846 patients: 283 patients in the imatinib 400 mg once daily group, 282 patients in the nilotinib dosage equivalent to DANZITEN 142 mg twice daily group, 281 patients in the nilotinib dosage equivalent to DANZITEN 190 mg twice daily group (an unapproved dosage regimen for this indication).
Median age was 46 years in the imatinib group and 47 years in the nilotinib group, with 12% and 13% of patients greater than or equal to 65 years of age in imatinib 400 mg once daily and nilotinib dosage equivalent to DANZITEN 142 mg twice daily treatment groups, respectively. There were slightly more male than female patients in all groups (56% and 56%, in imatinib 400 mg once daily and nilotinib dosage equivalent to DANZITEN 142 mg twice daily treatment groups). Approximately 60% of all patients were White, and 25% were Asian.
The primary data analysis was performed when all 846 patients completed 12 months of treatment (or discontinued earlier). Subsequent analyses were done when patients completed 24, 36, 48, and 60 months of treatment (or discontinued earlier). The median time on treatment was approximately 61 months in all three treatment groups.
The primary efficacy endpoint was major molecular response (MMR) at 12 months after the start of study medication. MMR was defined as less than or equal to 0.1% BCR-ABL/ABL % by international scale measured by RQ-PCR, which corresponds to a greater than or equal to 3 log reduction of BCR-ABL transcript from standardized baseline. Efficacy endpoints are summarized in Table 13.
Two patients in the nilotinib arm progressed to either accelerated phase or blast crisis (both within the first 6 months of treatment) while 12 patients on the imatinib arm progressed to either accelerated phase or blast crisis (7 patients within first 6 months, 2 patients within 6 to 12 months, 2 patients within 12 to 18 months and 1 patient within 18 to 24 months).
Table 13. Efficacy (MMR and CCyR) of Nilotinib Compared to imatinib in Adult Newly Diagnosed Ph+ CML-CP (ENESTnd)

 | Nilotinib 300 mg Twice Daily* | Imatinib 400 mg Once Daily
 | N = 282 | N = 283
MMR at 12 months (95% CI) | 44% (38.4, 50.3) | 22% (17.6, 27.6)
P-Valuea | < 0.0001
CCyRb by 12 months (95% CI) | 80% (75.0, 84.6) | 65% (59.2, 70.6)
MMR at 24 months (95% CI) | 62% (55.8, 67.4) | 38% (31.8, 43.4)
CCyRb by 24 months (95% CI) | 87% (82.4, 90.6) | 77% (71.7, 81.8)

Abbreviation: CI, confidence interval.
* Equivalent to DANZITEN 142 mg twice daily.
aCMH test stratified by Sokal risk group.
bCCyR: 0% Ph+ metaphases. Cytogenetic responses were based on the percentage of Ph+ metaphases among greater than or equal to 20 metaphase cells in each bone marrow sample.
By 60 months, MMR was achieved by 77% of patients on nilotinib and 60% of patients on imatinib; MR4.5 was achieved by 53.5% of patients on nilotinib and 31.4% on imatinib. Median overall survival was not reached in either arm. At the time of the 60-month final analysis, the estimated survival rate was 93.7% for patients on nilotinib and 91.7% for patients on imatinib.

14.2 Adult Patients with Resistant or Intolerant Ph+ CML-CP and CML-AP

The effectiveness of 190 mg twice daily of DANZITEN (nilotinib) tablets for the treatment of adult patients with Ph+ CML- CP and Ph+ CML-AP resistant or intolerant to prior therapy that included imatinib has been established from an adequate and well-controlled study of Tasigna® (nilotinib) capsules, which has a different recommended dosage than DANZITEN. Below is a display of the results of Tasigna® (nilotinib) capsules in this adequate and well-controlled study.
Study CAMN107A2101 (referred to as Study A2101) (NCT00109707) was a single-arm, open-label, multicenter study conducted to evaluate the efficacy and safety of nilotinib (dosage equivalent to DANZITEN 190 mg twice daily) in patients with imatinib-resistant or -intolerant CML with separate cohorts for chronic and accelerated phase disease. The definition of imatinib resistance included failure to achieve a complete hematologic response (by 3 months), cytogenetic response (by 6 months) or major cytogenetic response (by 12 months) or progression of disease after a previous cytogenetic or hematologic response. Imatinib intolerance was defined as discontinuation of treatment due to toxicity and lack of a major cytogenetic response at time of study entry. At the time of data cut- off, 321 patients with CML-CP and 137 patients with CML-AP with a minimum follow-up of 24 months were enrolled. In this study, about 50% of CML-CP and CML-AP patients were males, over 90% (CML-CP) and 80% (CML-AP) were White, and approximately 30% were age 65 years or older.

Overall, 73% of patients were imatinib resistant while 27% were imatinib intolerant. The median time of prior imatinib treatment was approximately 32 (CML-CP) and 28 (CML-AP) months. Prior therapy included hydroxyurea in 85% of patients, interferon in 56% and stem cell or bone marrow transplant in 8%. The median highest prior imatinib dose was 600 mg per day for patients with CML-CP and CML-AP, and the highest prior imatinib dose was greater than or equal to 600 mg/day in 74% of all patients with 40% of patients receiving imatinib doses greater than or equal to 800 mg/day.

Median duration of nilotinib treatment was 18.4 months in patients with CML-CP and 8.7 months in patients with CML-AP.
The efficacy endpoint in CML-CP was unconfirmed major cytogenetic response (MCyR) which included complete and partial cytogenetic responses.
The efficacy endpoint in CML-AP was confirmed hematologic response (HR), defined as either a complete hematologic response (CHR) or no evidence of leukemia (NEL). The rates of response for CML-CP and CML- AP patients are reported in Table 14.
Median durations of response had not been reached at the time of data analysis.

Table 14. Efficacy of Nilotinib in Adult Resistant or Intolerant Ph+ CML-CP and CML-AP (Study A2101)

Cytogenetic Response Rate (Unconfirmed) (%)a | Chronic Phase (n = 321)
Major (95% CI) | 51% (46%–57%)
Complete (95% CI) | 37% (32%–42%)
Partial (95% CI) | 15% (11%–19%)
 | Accelerated Phase(n = 137)
Hematologic Response Rate (Confirmed) (95% CI)b | 39% (31%–48%)
Complete Hematologic Response Rate (95% CI) | 30% (22%–38%)
No Evidence of Leukemia (95% CI) | 9% (5%–16%)

aCytogenetic response criteria: Complete (0% Ph+ metaphases) or partial (1% to 35%). Cytogenetic responses were based on the percentage of Ph-positive metaphases among greater than or equal to 20 metaphase cells in each bone marrow sample.
bHematologic response = CHR + NEL (all responses confirmed after 4 weeks).
CHR (CML-CP): WBC less than 10 x 10^9/L, platelets less than 450,000/mm^3, no blasts or promyelocytes in peripheral blood, less than 5% myelocytes + metamyelocytes in bone marrow, less than 20% basophils in peripheral blood, and no extramedullary involvement. CHR (CML-AP): neutrophils greater than or equal to 1.5 x 10^9/L, platelets greater than or equal to 100 x 10^9/L, no myeloblasts in peripheral blood, myeloblasts less than 5% in bone marrow, and no extramedullary involvement.
NEL: same criteria as for CHR but neutrophils greater than or equal to 1.0 x 10^9/L and platelets greater than or equal to 20 x 10^9/L without transfusions or bleeding.

Adult Patients With Chronic Phase
The MCyR rate in 321 CML-CP patients was 51%. The median time to MCyR among responders was 2.8 months (range, 1 to 28 months). The median duration of MCyR cannot be estimated. The median duration of exposure on this single arm-trial was 18.4 months. Among the CML-CP patients who achieved MCyR, 62% of them had MCyR lasting more than 18 months. The CCyR rate was 37%.
Adult Patients With Accelerated Phase
The overall confirmed hematologic response rate in 137 patients with CML-AP was 39%. The median time to first hematologic response among responders was 1 month (range, 1 to 14 months). Among the CML-AP patients who achieved HR, 44% of them had a response lasting for more than 18 months.
After imatinib failure, 24 different BCR-ABL mutations were noted in 42% of chronic phase and 54% of accelerated phase CML patients who were evaluated for mutations.

14.3 Treatment Discontinuation in Newly Diagnosed Ph+ CML-CP Patients Who Have Achieved a Sustained Molecular Response (MR4.5)

The efficacy of DANZITEN (nilotinib) tablets treatment discontinuation in adult patients with newly diagnosed Ph+ CML-CP has been established from an adequate and well-controlled study of Tasigna® (nilotinib) capsules, which has a different recommended dosage than DANZITEN. Below is a display of the results of Tasigna® (nilotinib) capsules in this adequate and well-controlled study.
The ENESTfreedom (Evaluating Nilotinib Efficacy and Safety in clinical Trials-freedom) study (NCT01784068) is an open-label, multicenter, single-arm study, where 215 adult patients with Ph+ CML-CP treated with nilotinib in first-line for ≥ 2 years who achieved MR4.5 as measured with the MolecularMD MRDx® BCR-ABL Test were enrolled to continue nilotinib treatment for an additional 52 weeks (nilotinib consolidation phase).
Of the 215 patients, 190 patients (88.4%) entered the “Treatment-Free Remission” (TFR) phase after achieving a sustained molecular response (MR4.5) during the consolidation phase, defined by the following criteria:
• The 4 last quarterly assessments (taken every 12 weeks) were at least MR4 (BCR-ABL/ABL ≤ 0.01% IS), and maintained for 1 year
• The last assessment being MR4.5 (BCR-ABL/ABL ≤ 0.0032% IS)
• No more than two assessments falling between MR4 and MR4.5 (0.0032% IS < BCR-ABL/ABL ≤ 0.01% IS).
The median age of patients who entered the TFR phase was 55 years, 49.5% were females, and 21.1% of the patients were ≥ 65 years of age. BCR-ABL levels were monitored every 4 weeks during the first 48 weeks of the TFR phase. Monitoring frequency was intensified to every 2 weeks upon the loss of MR4.0. Biweekly monitoring ended at one of the following time points:
• Loss of MMR requiring patient to reinitiate nilotinib treatment
• When the BCR-ABL levels returned to a range between MR4.0 and MR4.5
• When the BCR-ABL levels remained lower than MMR for 4 consecutive measurements (8 weeks from initial loss of MR4.0).
Any patient with loss of MMR during the TFR phase reinitiated nilotinib at a dosage equivalent to DANZITEN 142 mg twice daily or at a reduced dose level equivalent to DANZITEN 190 mg once daily if required from the perspective of tolerance, within 5 weeks after the collection date of the blood sample demonstrating loss of MMR. Patients who required reinitiation of nilotinib treatment were monitored for BCR-ABL levels every 4 weeks for the first 24 weeks and then every 12 weeks thereafter in patients who regained MMR.
Efficacy was based on the 96-week analysis data cut-off date, by which time, 91 patients (47.9%) discontinued from the TFR phase due to loss of MMR, and 1 (0.5%), 1 (0.5%), 1 (0.5%) and 3 patients (1.6%) due to death from unknown cause, physician decision, lost to follow-up and subject decision, respectively. Among the 91 patients who discontinued the TFR phase due to loss of MMR, 88 patients restarted nilotinib treatment and 3 patients permanently discontinued from the study.
By the 96-week data cut-off of the 88 patients who restarted treatment due to loss of MMR in the TFR phase, 87 patients (98.9%) patients regained MMR (one patient discontinued study permanently due to subject decision after 7.1 weeks of retreatment without regaining MMR) and 81 patients (92.0%) regained MR4.5 by the time of the cut-off date. The cumulative rate of MMR and MR4.5 regained at 24 weeks since treatment reinitiation was 97.7% (86/88 patients) and 86.4% (76/88 patients), respectively.
Table 15. Efficacy Results for ENESTfreedom

Patients Who Entered the Treatment Free Remission (TFR) Phase (Full Analysis Set, N = 190)
 | Patients in TFR phase^1 at the specified time point |  | Loss of MMR^2 by the specified time point
 | % | 95% CI | %
24 weeks | 62.1 | (54.8, 69.0) | 35.8
48 weeks | 51.6 | (44.2, 58.9) | 45.8
96 weeks | 48.9 | (41.6, 56.3) | 47.9

Abbreviation: CI, confidence interval.
^1Patients in MMR at the specified time point in the TFR phase.
^2Based on the time to event (loss of MMR) data during the TFR phase.
Among the 190 patients in the TFR phase, 98 patients had a treatment-free survival (TFS) event (defined as discontinuation from TFR phase due to any reason, loss of MMR, death due to any cause, progression to AP/BC up to the end of TFR phase, or reinitiation of treatment due to any cause in the study) by the 96-week cut-off date.

Figure 1. Kaplan-Meier Estimate of Treatment-Free Survival After Start of TFR (Full Analysis Set ENESTfreedom)

1. For a given time point, the points on the dashed curves represent the 95% confidence limits for the associated KM estimate on the solid curve.
2. By the time of the 96-week data cut-off date, one single patient lost MMR at Week 120, at the time when only 8 patients were considered at risk. This explains the artificial drop at the end of the curve.

14.4 Treatment Discontinuation in Ph+ CML-CP Patients Who Have Achieved a Sustained Molecular Response (MR4.5) on DANZITEN Following Prior Imatinib Therapy

The efficacy of DANZITEN (nilotinib) tablets treatment discontinuation in adult patients with Ph+ CML-CP following prior imatinib has been established from an adequate and well-controlled study of Tasigna® (nilotinib) capsules. Below is a display of the results of Tasigna® (nilotinib) capsules in this adequate and well-controlled study.
The ENESTop (Evaluating Nilotinib Efficacy and Safety in clinical Trials-STop) study (NCT01698905) is an open-label, multicenter, single-arm study, where 163 adult patients with Ph+ CML-CP taking tyrosine kinase inhibitors (TKIs) for ≥ 3 years (imatinib as initial TKI therapy for more than 4 weeks without documented MR4.5 on imatinib at the time of switch to nilotinib, then switched to nilotinib for at least 2 years), and who achieved MR4.5 on nilotinib treatment as measured with the MolecularMD MRDx® BCR-ABL Test were enrolled to continue nilotinib treatment for an additional 52 weeks (nilotinib consolidation phase). Of the 163 patients, 126 patients (77.3%) entered the TFR phase after achieving a sustained molecular response (MR4.5) during the consolidation phase, defined by the following criterion:
• The 4 last quarterly assessments (taken every 12 weeks) showed no confirmed loss of MR4.5 (BCR- ABL/ABL ≤ 0.0032% IS) during 1 year.
The median age of patients who entered the TFR phase was 56 years, 55.6% were females, and 27.8% of the patients were ≥ 65 years of age. The median actual dose intensity during the 52-week nilotinib consolidation phase was 771.8 mg/day with 52.4%, 29.4%, 0.8%, 16.7%, and 0.8% of patients receiving a daily nilotinib dosage equivalent to DANZITEN 380 mg, 284 mg, 213 mg, 190 mg and 142 mg just before entry into the TFR phase, respectively.
Patients who entered the TFR phase but experienced two consecutive measurements of BCR-ABL/ABL > 0.01% IS were considered having a confirmed loss of MR4.0, triggering reinitiation of nilotinib treatment. Patients with loss of MMR in the TFR phase immediately restarted nilotinib treatment without confirmation. All patients who restarted nilotinib therapy had BCR-ABL transcript levels monitored every 4 weeks for the first 24 weeks, then once every 12 weeks.
Efficacy was based on the 96-week analysis data cut-off date, by which time, 61 patients (48.4%) had discontinued from the TFR phase: 58 patients (46.0%) due to loss of MMR or confirmed loss of MR4.0, 2 patients (1.6%) due to subject/guardian decision and one patient (0.8%) due to pregnancy. Among the 58 patients who discontinued from the TFR phase due to confirmed loss of MR4.0 or loss of MMR, 56 patients restarted Nilotinib therapy and 2 patients permanently discontinued from the study.
By the 96-week data cut-off, of the 56 patients who restarted nilotinib treatment due to confirmed loss of MR4.0 or loss of MMR in the TFR phase, 52 patients (92.9%) regained MR4.0 and MR4.5; 4 patients (7.1%) did not regain MR4.0 by the time of the cut-off date. The cumulative rate of MR4 and MR4.5 regained by 48-weeks since treatment reinitiation, was 92.9% (52/56 patients) and 91.1% (51/56 patients), respectively.
Table 16. Efficacy Results for ENESTop

Patients Who Entered the Treatment Free Remission (TFR) Phase (Full Analysis Set, N = 126)
 | Patients in TFR phase^1 at the specified time point |  | Loss of MMR or confirmed loss of MR4^2 by the specified time point
 | % | 95% CI | %
24 weeks | 60.3 | (51.2, 68.9) | 38.9
48 weeks | 57.9 | (48.8, 66.7) | 41.3
96 weeks | 53.2 | (44.1, 62.1) | 43.7

Abbreviation: CI, confidence interval.

^1Patients without loss of MMR or confirmed loss of MR4 by specified time point of TFR phase.
^2Based on the time to event (loss of MMR or confirmed loss of MR4) data during the TFR phase.

Among the 126 patients in the TFR phase, 61 patients (48.4%) had a treatment-free survival (TFS) event (defined as discontinuation from TFR phase due to any reason, loss of MMR, confirmed loss of MR4, death due to any cause, progression to AP/BC up to the end of TFR phase, or reinitiation of treatment due to any cause in the study) on or before the 96-month cut-off date.
Figure 2: Kaplan-Meier Estimate of Treatment-Free Survival after Start of TFR (Full Analysis Set ENESTop)

1. For a given time point, the points on the dashed curves represent the 95% confidence limits for the associated KM estimate on the solid curve.

Additional pediatric use information is approved for Novartis Pharmaceuticals Corporation’s Tasigna® (nilotinib) capsules. However, due to Novartis Pharmaceuticals Corporation’s marketing exclusivity rights, this drug product is not labeled with that pediatric information.

16 HOW SUPPLIED/STORAGE AND HANDLING

DANZITEN (nilotinib) 71 mg tablets are pink, coated, oblong tablets, debossed with “N5” on one side and plain on other side. DANZITEN (nilotinib) 95 mg tablets are yellow, coated, oblong tablets, debossed with “N2” on one side and plain on other side. DANZITEN (nilotinib) 71 mg and 95 mg tablets are supplied in blister packs.

71 mg

Outer Carton containing 4 inner carton packs (4x28)...............................NDC 24338-154-01
Inner carton containing 2 blister packs (2x14)..........................................NDC 24338-154-02
Blisters of 14 tablets (1x14)......................................................................NDC 24338-154-03
95 mg
Outer Carton containing 4 inner carton packs (4x28)...............................NDC 24338-155-01
Inner carton containing 2 blister packs (2x14)..........................................NDC 24338-155-02
Blisters of 14 tablets (1x14)......................................................................NDC 24338-155-03

Store at 20°C to 25°C (68°F to 77°F); excursions permitted between 15°C and 30°C (59°F and 86°F) [see USP Controlled Room Temperature].

17 PATIENT COUNSELING INFORMATION

Advise the patient to read the FDA-approved patient labeling (Medication Guide).

Taking DANZITEN
Advise patients that DANZITEN may not be substitutable, on a milligram per milligram basis, with other nilotinib products. Advise patients to take DANZITEN exactly as prescribed [see Warnings and Precautions (5.1)].
Advise patients to take DANZITEN doses twice daily approximately 12 hours apart. Advise patients to swallow the tablets whole with water and not to cut, crush, or chew the tablets.
Advise patients to take DANZITEN with or without food. Patients should not consume grapefruit products and other foods that are known to inhibit CYP3A4 at any time during DANZITEN treatment [see Dosage and Administration (2.2), Drug Interactions (7.1)].
If the patient misses a dose of DANZITEN, the patient should take the next scheduled dose at its regular time. The patient should not take two doses at the same time.
Compliance
Advise patients of the following:
• Continue taking DANZITEN every day for as long as their doctor tells them.
• This is a long-term treatment.
• Do not change dose or stop taking DANZITEN without first consulting their doctor.

Myelosuppression
Advise patients that treatment with nilotinib can cause serious thrombocytopenia, neutropenia, and anemia. Advise patients to seek immediate medical attention if symptoms suggestive of low blood counts occur, such as fever, chills or other signs of infection, unexplained bleeding or bruising, or unexplained weakness or shortness of breath [see Warnings and Precautions (5.2)].
QT Prolongation
Advise patients that nilotinib can cause possibly life-threatening, abnormal heartbeat. Advise patients to seek immediate medical attention if symptoms of abnormal heartbeat occur, such as feeling light-headed, faint or experiencing an irregular heartbeat [see Warnings and Precautions (5.3)].
Cardiac and Arterial Vascular Occlusive Events
Advise patients that cardiovascular events (including ischemic heart disease, peripheral arterial occlusive disease, and ischemic cerebrovascular events) have been reported. Advise patients to seek immediate medical attention if any symptoms suggestive of a cardiovascular event occur, such as chest or leg pain, numbness or weakness, or problems walking or speaking occur suddenly [see Warnings and Precautions (5.5)].
Pancreatitis and Elevated Serum Lipase
Advise patients that nilotinib can increase the risk of pancreatitis and that patients with a previous history of pancreatitis may be at greater risk. Advise patients to seek immediate medical attention if symptoms suggestive of pancreatitis occur, such as sudden stomach area pain with accompanying nausea and vomiting [see Warnings and Precautions (5.6)].
Hepatotoxicity
Advise patients that nilotinib can increase the risk of hepatotoxicity and that patients with previous history of liver diseases may be at risk. Advise patients to seek immediate medical attention if any symptoms suggestive of hepatotoxicity occur, such as stomach pain, yellow skin and eyes, and dark-colored urine [see Warnings and Precautions (5.7)].
Tumor Lysis Syndrome
Advise patients that nilotinib can cause TLS and to seek immediate medical attention if any symptoms suggestive of TLS occur, such as an abnormal heartbeat or less urine production [see Warnings and Precautions (5.9)].
Hemorrhage
Advise patients that serious hemorrhagic events, including fatal events, have occurred in patients with CML treated with nilotinib. Advise patients to seek immediate medical attention if symptoms suggestive of hemorrhage occur, such as uncontrolled bleeding, changes in eyesight, unconsciousness, or sudden headache or sudden confusion in surroundings [see Warnings and Precautions (5.10)].
Fluid Retention
Advise patients that nilotinib can cause fluid retention and to seek immediate medical attention if any symptoms suggestive of fluid retention, such as shortness of breath, rapid weight gain, or swelling occur [see Warnings and Precautions (5.13)].
Effects on Growth and Development in Pediatric Patients
Inform pediatric patients and their caregivers of the possibility of developing growth abnormalities. Growth retardation has been reported in pediatric patients treated with nilotinib. Therefore, monitor growth and development in pediatric patients [see Warnings and Precautions (5.14)].
Treatment-Free Remission (TFR)
Advise patients that frequent monitoring is required to detect possible loss of remission if TFR is attempted. Advise patients that musculoskeletal symptoms, such as muscle pain, pain in extremity, joint pain, bone pain, or spinal pain, may occur more frequently than before treatment discontinuation [see Warnings and Precautions (5.16)].
Embryo-Fetal Toxicity
Advise pregnant women of the potential risk to a fetus. Advise females of reproductive potential to inform their healthcare provider of a known or suspected pregnancy [see Warnings and Precautions (5.15), Use in Specific Populations (8.1)].
Advise females of reproductive potential to use effective contraception during treatment and for 14 days after receiving the last dose of DANZITEN [see Use in Specific Populations (8.3)].
Lactation
Advise women not to breastfeed during treatment with DANZITEN and for 14 days after the last dose [see Use in Specific Populations (8.2)].
Drug Interactions
Advise patients that DANZITEN and certain other medicines, including over the counter medications or herbal supplements (such as St. John’s Wort), can interact with each other [see Drug Interactions (7)].
Manufactured for:
Azurity Pharmaceuticals, Inc.
Woburn, MA 01801

Medication Guide
DANZITEN (dan-zi-ten)
(nilotinib)
tablets

What is the most important information I should know about DANZITEN?
DANZITEN can cause a possible life-threatening heart problem called QTc prolongation. QTc prolongation causes an irregular heartbeat, which may lead to sudden death.
Your healthcare provider should check the electrical activity of your heart with a test called an electrocardiogram (ECG):
• before starting DANZITEN
• with any dose changes
• 7 days after starting DANZITEN
• regularly during DANZITEN treatment
You may lower your chances for having QTc prolongation with Nilotinib if you:
• Do not drink grapefruit juice, eat grapefruit, or take supplements containing grapefruit extract during treatment with DANZITEN.Grapefruit products increase the amount of Nilotinib in your body.
• Avoid taking other medicines or supplements with Nilotinib that can also cause QTc prolongation.
• Nilotinib can interact with many medicines and supplements and increase your chance for serious and life-threatening side effects.
• Do not take any other medicine during treatment with DANZITEN unless your healthcare provider tells you it is okay to do so.
• For more information, see “How should I take DANZITEN?”
Call your healthcare provider right away if you feel lightheaded, faint, or have an irregular heartbeat during treatment with DANZITEN. These can be symptoms of QTc prolongation.
See “What are the possible side effects of DANZITEN? for more information about side effects.

What is DANZITEN?
DANZITEN is a prescription medicine used to treat:
• adults who have been newly diagnosed with a certain type of leukemia called Philadelphia chromosome positive chronic myeloid leukemia (Ph+ CML) in chronic phase.
• adults with chronic phase Ph+ CML or accelerated phase Ph+ CML who:
o are no longer benefiting from other treatments, including imatinib (Gleevec), or
o have taken other treatments, including imatinib (Gleevec), and cannot tolerate them.
It is not known if nilotinib is safe and effective in children younger than 1 year of age with newly diagnosed, resistant, or intolerant Ph+ CML in chronic phase.
The long-term effects of treating children with nilotinib for a long period of time are not known.

Who should not take DANZITEN?
Do not take if you have:
• low levels of potassium or magnesium in your blood
• long QTc syndrome

Before taking DANZITEN, tell your healthcare provider about all of your medical conditions, including if you:
• have heart problems
• have had a stroke or other problems due to decreased blood flow to the brain
• have problems with decreased blood flow to your legs
• have irregular heartbeat
• have QTc prolongation or a family history of it
• have liver problems
• have had pancreatitis
• have low blood levels of potassium or magnesium in your blood
• have bleeding problems
• had a surgical procedure involving the removal of the entire stomach (total gastrectomy)
• are pregnant or plan to become pregnant. Nilotinib can harm your unborn baby. Tell your healthcare provider right away if you are pregnant, or if you become pregnant during treatment with DANZITEN.
In females who are able to become pregnant:
• Your healthcare provider should do a pregnancy test before you start treatment with DANZITEN.
• Use effective birth control (contraception) during treatment with DANZITEN and for 14 days after the last dose.
• are breastfeeding or plan to breastfeed. It is not known if Nilotinib passes into your breast milk. Do not breastfeed during treatment and for 14 days after your last dose of DANZITEN.
Tell your healthcare provider about all the medicines you take, including prescription and over-the-counter medicines, vitamins and herbal supplements.
If you need to take antacids (medicines to treat heartburn) do not take them at the same time that you take DANZITEN. If you take:
• a medicine to block the amount of acid produced in the stomach (H2 blocker): Take these medicines about 10 hours before you take DANZITEN, or about 2 hours after you take DANZITEN.
• an antacid that contains aluminum hydroxide, magnesium hydroxide, and simethicone to reduce the amount of acid in the stomach: Take these medicines about 2 hours before or about 2 hours after you take DANZITEN.
Nilotinib can interact with many medicines and supplements and increase your chance for serious and life-threatening side effects. See “What is the most important information I should know about DANZITEN?”

How should I take DANZITEN?
• Do not switch from DANZITEN to other medicines that contain nilotinib without talking to your healthcare provider. The amount of nilotinib in a dose of DANZITEN may not be the same as the amount in other medicines that contain nilotinib.
• Take DANZITEN exactly as your healthcare provider tells you to take it. • Do not change your dose or stop taking DANZITEN unless your healthcare provider tells you.
• DANZITEN is a long-term treatment.
• Take your prescribed dose of DANZITEN 2 times a day, about 12 hours apart.
• Swallow DANZITEN tablets whole with water. Do not cut, crush, or chew the tablets. If you cannot swallow DANZITEN whole, tell your healthcare provider.
• Take DANZITEN with or without food.
• Do not drink grapefruit juice, eat grapefruit, or take supplements containing grapefruit extract at any time during treatment. See “What is the most important information I should know about DANZITEN?”
• If you miss a dose, just take your next dose at your regular time. Do not take 2 doses at the same time to make up for a missed dose.
• If you take too much DANZITEN, call your healthcare provider or go to the nearest hospital emergency room right away. Symptoms may include vomiting and drowsiness.
• During treatment with DANZITEN your healthcare provider will do tests to check for side effects and to see how well DANZITEN is working for you. The tests will check your:
o heart
o blood cells (white blood cells, red blood cells, and platelets). Your blood cells should be checked every 2 weeks for the first 2 months and then monthly.
o electrolytes (potassium, magnesium)
o pancreas and liver function
o bone marrow samples
Your healthcare provider may change your dose. Your healthcare provider may have you stop DANZITEN for some time or lower your dose if you have side effects with it.
• Your healthcare provider will monitor your CML during treatment with DANZITEN to see if you are in a remission. After at least 3 years of treatment with DANZITEN, your healthcare provider may do certain tests to determine if you continue to be in remission. Based on your test results, your healthcare provider may decide if you may be eligible to try stopping treatment with DANZITEN. This is called Treatment Free Remission (TFR).
• Your healthcare provider will carefully monitor your CML during and after you stop taking DANZITEN. Based on your test results, your healthcare provider may need to re-start your DANZITEN if your CML is no longer in remission.
• It is important that you are followed by your healthcare provider and undergo frequent monitoring to find out if you need to re-start your DANZITEN treatment because you are no longer in TFR. Follow your healthcare provider’s instructions about re-starting DANZITEN if you are no longer in TFR.

What are the possible side effects of DANZITEN?
DANZITEN may cause serious side effects, including:
• See “What is the most important information I should know about DANZITEN?”
• Low blood cell counts. Low blood cell counts (red blood cells, white blood cells, and platelets) are common with DANZITEN, but can also be severe. Your healthcare provider will check your blood counts regularly during treatment with DANZITEN. Call your healthcare provider or get medical help right away if you develop any signs or symptoms of low blood counts, including:
o fever
o chills or other signs of infection
o unexplained bleeding or bruising
o unexplained weakness
o shortness of breath
• Decreased blood flow to the leg, heart, or brain. People who have recently been diagnosed with Ph+ CML and take DANZITEN may develop decreased blood flow to the leg, the heart, or brain.
Get medical help right away if you suddenly develop any of the following symptoms:
• chest pain or discomfort
• numbness or weakness
• problems walking or speaking
• leg pain
• your leg feels cold
• change in the skin color of your leg
• Pancreas inflammation (pancreatitis). Tell your healthcare provider right away if you develop any symptoms of pancreatitis, including sudden stomach area pain with nausea and vomiting.
• Liver problems.DANZITEN can increase your risk of liver problems. People who have had liver problems in the past may be at risk for getting liver problems with DANZITEN. Call your healthcare provider or get medical help right away if you develop any symptoms of liver problems, including:
• stomach area (abdominal) pain • yellow skin and eyes • dark-colored urine
• Tumor Lysis Syndrome (TLS). TLS is caused by a fast breakdown of cancer cells. Your healthcare provider may do blood tests to check you for TLS. TLS can cause you to have:
○ kidney failure and the need for dialysis treatment
○ an abnormal heartbeat
• Bleeding problems. Serious bleeding problems and death have happened during treatment with DANZITEN. Tell your healthcare provider right away if you develop any signs and symptoms of bleeding during treatment with DANZITEN.
• Fluid retention. Your body may hold too much fluid (fluid retention). Symptoms of fluid retention include shortness of breath, rapid weight gain, and swelling.
• Abnormal growth or development in children. Effects on growth and development have happened in children with chronic phase Ph+ CML during treatment with nilotinib. Some children and adolescents may have slower than normal growth during treatment with nilotinib.
The most common side effects of DANZITEN in adults include:
• nausea • diarrhea
• rash • cough
• headache • constipation
• tiredness • muscle and joint pain
• itching • runny or stuffy nose, sneezing, sore throat
• vomiting • fever
• night sweats
Side effects in adult patients attempting treatment free remission:
If you and your healthcare provider decide that you can stop taking DANZITEN and try treatment free remission (TFR), you may have more muscle and bone (musculoskeletal) symptoms than before you stopped treatment. Symptoms may include:
• muscle pain • bone pain
• arm and leg pain • spine pain
• joint pain
Tell your healthcare provider if you have any side effect that bothers you or does not go away. These are not all of the possible side effects of DANZITEN.
Call your doctor for medical advice about side effects. You may report side effects to FDA at 1-800-FDA-1088.

How should I store DANZITEN?
• Store DANZITEN at room temperature between 68°F to 77°F (20°C to 25°C).
• Safely throw away medicine that is out of date or no longer needed.
Keep DANZITEN and all medicines out of the reach of children.

General information about the safe and effective use of DANZITEN.
Medicines are sometimes prescribed for purposes other than those listed in a Medication Guide. Do not use DANZITEN for a condition for which it was not prescribed. Do not give DANZITEN to other people, even if they have the same symptoms that you have. It may harm them. You can ask your pharmacist or healthcare provider for information about DANZITEN that is written for health professionals.

What are the ingredients in DANZITEN?
Active ingredient: nilotinib tartrate
Inactive ingredients: colloidal silicon dioxide, croscarmellose sodium, hypromellose acetate succinate, iron oxide red (in 71 mg strength tablets), iron oxide yellow (in 95 mg strength tablets), magnesium stearate, microcrystalline cellulose, polyethylene glycol, polyvinyl alcohol, talc, and titanium dioxide.
Additional pediatric use information is approved for Novartis Pharmaceuticals Corporation’s Tasigna® (nilotinib) capsules. However, due to Novartis Pharmaceuticals Corporation’s marketing exclusivity rights, this drug product is not labeled with that pediatric information.
Manufactured for:
Azurity Pharmaceuticals, Inc.
Woburn, MA 01801

This Medication Guide has been approved by the U.S. Food and Drug Administration. Issued: 11/2024

PACKAGE LABEL.PRINCIPAL DISPLAY PANEL

NDC 24338-154-01

DANZITEN (nilotinib) tablets 71 mg - Outer Carton Label

Outer Carton containing 4 inner carton packs (4x28)

71 mg per tablet

NDC 24338-154-02

DANZITEN (nilotinib) tablets 71 mg - Inner Carton Label

Carton of 2 blister packs (2x14)

71 mg per tablet

Package Label Principal Display Panel

NDC 24338-155-01

DANZITEN (nilotinib) tablets 95 mg - Outer Carton Label

Outer Carton containing 4 inner carton packs (4x28)

95 mg per tablet

NDC 24338-155-02

DANZITEN (nilotinib) tablets 95 mg - Inner Carton Label

Carton of 2 blister packs (2x14)

95 mg per tablet